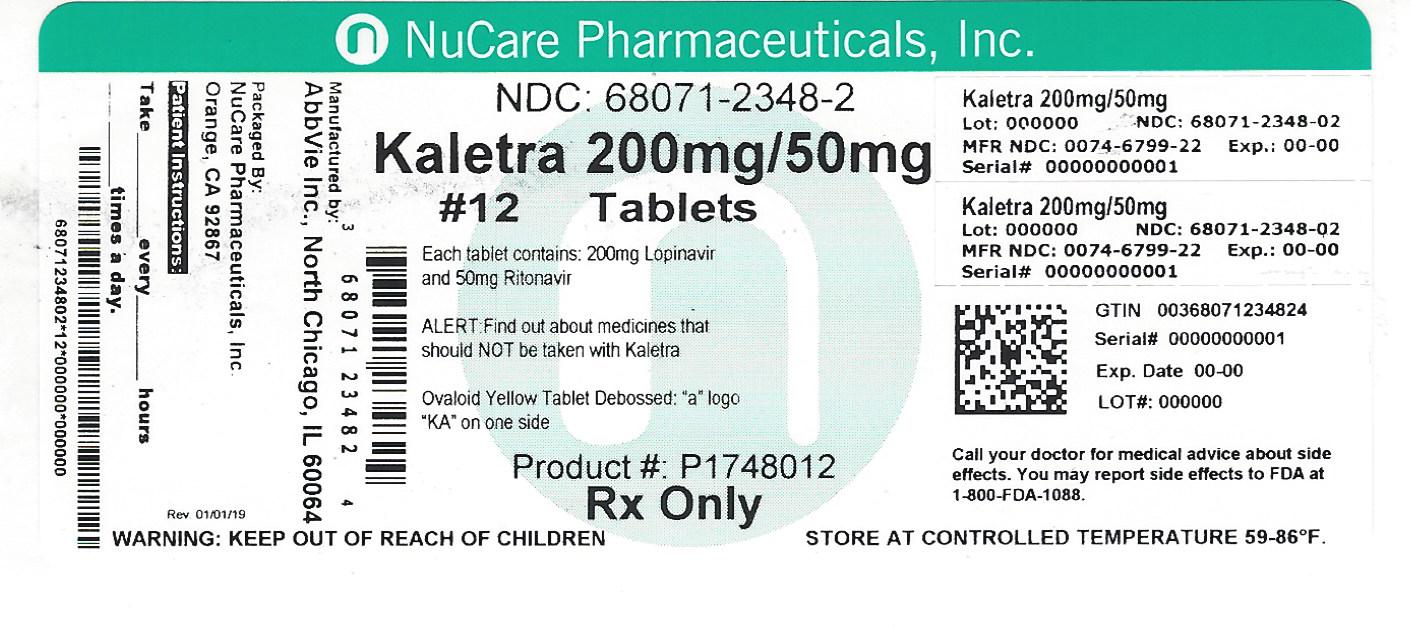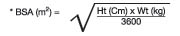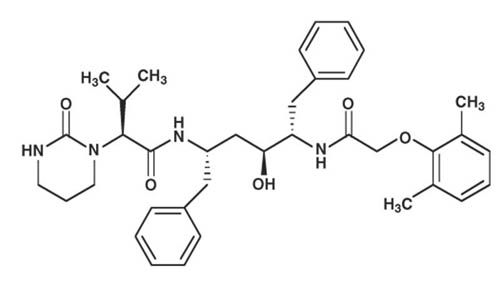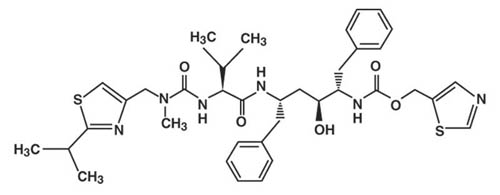 DRUG LABEL: Kaletra
NDC: 68071-2348 | Form: TABLET, FILM COATED
Manufacturer: NuCare Pharmaceuticals,Inc.
Category: prescription | Type: HUMAN PRESCRIPTION DRUG LABEL
Date: 20230706

ACTIVE INGREDIENTS: LOPINAVIR 200 mg/1 1; RITONAVIR 50 mg/1 1
INACTIVE INGREDIENTS: COPOVIDONE K25-31; SORBITAN MONOLAURATE; SODIUM STEARYL FUMARATE; TITANIUM DIOXIDE; POLYETHYLENE GLYCOL 400; TALC; POLYETHYLENE GLYCOL 3350; FERRIC OXIDE YELLOW; POLYSORBATE 80; SILICON DIOXIDE; HYPROMELLOSE, UNSPECIFIED; HYDROXYPROPYL CELLULOSE (1600000 WAMW)

HIGHLIGHTS OF PRESCRIBING INFORMATION

These highlights do not include all the information needed to use KALETRA safely and effectively. See full prescribing information for KALETRA.
KALETRA (lopinavir and ritonavir) tablet, for oral use
KALETRA (lopinavir and ritonavir) oral solution
Initial U.S. Approval: 2000

RECENT MAJOR CHANGES

Contraindications (4) | 12/2019

1 INDICATIONS AND USAGE

KALETRA is an HIV-1 protease inhibitor indicated in combination with other antiretroviral agents for the treatment of HIV-1 infection in adults and pediatric patients (14 days and older). (1)

2 DOSAGE AND ADMINISTRATION

Tablets: May be taken with or without food, swallowed whole and not chewed, broken, or crushed. (2.1)

Oral solution: must be taken with food. (2.1)

KALETRA oral solution is not recommended for use with polyurethane feeding tubes due to potential incompatibility. Feeding tubes composed of silicone or polyvinyl chloride (PVC) can be used. (2.2)

Adults (2.3):

- Total recommended daily dosage is 800/200 mg given once or twice daily.
- KALETRA can be given as once daily or twice daily regimen. See Full Prescribing Information for details.
- KALETRA once daily dosing regimen is not recommended in:
  - Adult patients with three or more of the following lopinavir resistance-associated substitutions: L10F/I/R/V, K20M/N/R, L24I, L33F, M36I, I47V, G48V, I54L/T/V, V82A/C/F/S/T, and I84V. (12.4)
  - In combination with carbamazepine, phenobarbital, or phenytoin. (7.3)
  - In combination with efavirenz, nevirapine, or nelfinavir. (12.3)
  - In pregnant women. (2.5, 8.1, 12.3)

Pediatric Patients (14 days and older) (2.4):

- KALETRA once daily dosing regimen is not recommended in pediatric patients.
- Twice daily dose is based on body weight or body surface area.

Concomitant Therapy in Adults and Pediatric Patients:

- Dose adjustments of KALETRA may be needed when co-administering with efavirenz, nevirapine, or nelfinavir. (2.3, 2.4, 7.3)
- KALETRA oral solution should not be administered to neonates before a postmenstrual age (first day of the mother’s last menstrual period to birth plus the time elapsed after birth) of 42 weeks and a postnatal age of at least 14 days has been attained (2.4, 5.2)

Pregnancy (2.5):

- 400/100 mg twice daily in pregnant patients with no documented lopinavir-associated resistance substitutions.

- There are insufficient data to recommend a KALETRA dose for pregnant patients with any documented KALETRA-associated resistance substitutions.
- No dose adjustment of KALETRA is required for patients during the postpartum period.

3 DOSAGE FORMS AND STRENGTHS

- Tablets: 200 mg lopinavir and 50 mg ritonavir (3)
- Tablets: 100 mg lopinavir and 25 mg ritonavir (3)
- Oral solution: 80 mg lopinavir and 20 mg ritonavir per milliliter (3)

4 CONTRAINDICATIONS

- Hypersensitivity to KALETRA (e.g., toxic epidermal necrolysis, Stevens-Johnson syndrome, erythema multiforme, urticaria, angioedema) or any of its ingredients, including ritonavir. (4)
- Co-administration with drugs highly dependent on CYP3A for clearance and for which elevated plasma levels may result in serious and/or life-threatening events. (4)
- Co-administration with potent CYP3A inducers where significantly reduced lopinavir plasma concentrations may be associated with the potential for loss of virologic response and possible resistance and cross resistance. (4)

5 WARNINGS AND PRECAUTIONS

The following have been observed in patients receiving KALETRA:

- The concomitant use of KALETRA and certain other drugs may result in known or potentially significant drug interactions. Consult the full prescribing information prior to and during treatment for potential drug interactions. (5.1, 7.3)
- Toxicity in preterm neonates: KALETRA oral solution should not be used in preterm neonates in the immediate postnatal period because of possible toxicities. A safe and effective dose of KALETRA oral solution in this patient population has not been established. (2.4, 5.2)
- Pancreatitis: Fatalities have occurred; suspend therapy as clinically appropriate. (5.3)
- Hepatotoxicity: Fatalities have occurred. Monitor liver function before and during therapy, especially in patients with underlying hepatic disease, including hepatitis B and hepatitis C, or marked transaminase elevations. (5.4, 8.6)
- QT interval prolongation and isolated cases of torsade de pointes have been reported although causality could not be established. Avoid use in patients with congenital long QT syndrome, those with hypokalemia, and with other drugs that prolong the QT interval. (5.1, 5.5, 12.3)
- PR interval prolongation may occur in some patients. Cases of second and third degree heart block have been reported. Use with caution in patients with pre-existing conduction system disease, ischemic heart disease, cardiomyopathy, underlying structural heart disease or when administering with other drugs that may prolong the PR interval. (5.1, 5.6, 12.3)
- Patients may develop new onset or exacerbations of diabetes mellitus, hyperglycemia (5.7), immune reconstitution syndrome. (5.8), redistribution/accumulation of body fat. (5.10)
- Total cholesterol and triglycerides elevations. Monitor prior to therapy and periodically thereafter. (5.9)
- Hemophilia: Spontaneous bleeding may occur, and additional factor VIII may be required. (5.11)

6 ADVERSE REACTIONS

Commonly reported adverse reactions to KALETRA included diarrhea, nausea, vomiting, hypertriglyceridemia and hypercholesterolemia. (6.1)
To report SUSPECTED ADVERSE REACTIONS, contact AbbVie Inc. at 1-800-633-9110 or FDA at 1-800-FDA-1088 or www.fda.gov/medwatch

7 DRUG INTERACTIONS

Co-administration of KALETRA can alter the plasma concentrations of other drugs and other drugs may alter the plasma concentrations of lopinavir. The potential for drug-drug interactions must be considered prior to and during therapy. (4, 5.1, 7, 12.3)

8 USE IN SPECIFIC POPULATIONS

Lactation: Breastfeeding not recommended. (8.2)

FULL PRESCRIBING INFORMATION

1 INDICATIONS AND USAGE

KALETRA is indicated in combination with other antiretroviral agents for the treatment of HIV-1 infection in adults and pediatric patients 14 days and older.

Limitations of Use:

- Genotypic or phenotypic testing and/or treatment history should guide the use of KALETRA. The number of baseline lopinavir resistance-associated substitutions affects the virologic response to KALETRA [see Microbiology (12.4)] .

2 DOSAGE AND ADMINISTRATION

2.1 General Administration Recommendations

KALETRA tablets may be taken with or without food. The tablets should be swallowed whole and not chewed, broken, or crushed. KALETRA oral solution must be taken with food.

2.2 Administering Oral Solution by Feeding Tube

Because KALETRA oral solution contains ethanol and propylene glycol, it is not recommended for use with polyurethane feeding tubes due to potential incompatibility. Feeding tubes that are compatible with ethanol and propylene glycol, such as silicone and polyvinyl chloride (PVC) feeding tubes, can be used for administration of KALETRA oral solution. Follow instructions for use of the feeding tube to administer the medicine.

2.3 Dosage Recommendations in Adults

KALETRA can be given in once daily or twice daily dosing regimen at dosages noted in Tables 1 and 2. KALETRA once daily dosing regimen is not recommended in:

- Adult patients with three or more of the following lopinavir resistance-associated substitutions: L10F/I/R/V, K20M/N/R, L24I, L33F, M36I, I47V, G48V, I54L/T/V, V82A/C/F/S/T, and I84V [see Microbiology (12.4)] .
- In combination with carbamazepine, phenobarbital, or phenytoin [see Drug Interactions (7.3)] .
- In combination with efavirenz, nevirapine, or nelfinavir [see Drug Interactions (7.3) and Clinical Pharmacology (12.3)] .
- In pediatric patients younger than 18 years of age [see Dosage and Administration (2.4)] .
- In pregnant women [see Dosage and Administration (2.5), Use in Specific Populations (8.1) and Clinical Pharmacology (12.3)] .

Table 1. Recommended Dosage in Adults - KALETRA Once Daily Regimen
KALETRA Dosage Form | Recommended Dosage
200 mg/50 mg Tablets | 800 mg/200 mg (4 tablets) once daily
80 mg/20 mg per mL Oral Solution | 800 mg/200 mg (10 mL) once daily

Table 2. Recommended Dosage in Adults - KALETRA Twice Daily Regimen
KALETRA Dosage Form | Recommended Dosage
200 mg/50 mg Tablets | 400 mg/100 mg (2 tablets) twice daily
80 mg/20 mg per mL Oral Solution | 400 mg/100 mg (5 mL) twice daily

The dose of KALETRA must be increased when administered in combination with efavirenz, nevirapine or nelfinavir. Table 3 outlines the dosage recommendations for twice daily dosing when KALETRA is taken in combination with these agents.

Table 3. Recommended Dosage in Adults - KALETRA Twice Daily Regimen in Combination with Efavirenz, Nevirapine, or Nelfinavir
KALETRA Dosage Form | Recommended Dosage
200 mg/50 mg Tablets and 100 mg/25 mg Tablets | 500 mg/125 mg (2 tablets of 200 mg/50 mg + 1 tablet of 100 mg/25 mg) twice daily
80 mg/20 mg per mL Oral Solution | 520 mg/130 mg (6.5 mL) twice daily

2.4 Dosage Recommendations in Pediatric Patients

KALETRA tablets and oral solution are not recommended for once daily dosing in pediatric patients younger than 18 years of age. The dose of the oral solution should be administered using the calibrated cup (supplied) or oral dosing syringe. KALETRA 100/25 mg tablets should be considered only in children who have reliably demonstrated the ability to swallow the intact tablet.

KALETRA oral solution is not recommended in neonates before a postmenstrual age (first day of the mother’s last menstrual period to birth plus the time elapsed after birth) of 42 weeks and a postnatal age of at least 14 days has been attained [see Warnings and Precautions (5.2)] .

KALETRA oral solution contains approximately 42% (v/v) ethanol and approximately 15% (w/v) propylene glycol. Total amounts of ethanol and propylene glycol from all medicines that are to be given to pediatric patients 14 days to 6 months of age should be taken into account in order to avoid toxicity from these excipients [see Warnings and Precautions (5.2) and Overdosage (10)].

Pediatric Dosage Calculations

Calculate the appropriate dose of KALETRA for each individual pediatric patient based on body weight (kg) or body surface area (BSA) to avoid underdosing or exceeding the recommended adult dose.

Body surface area (BSA) can be calculated as follows:

The KALETRA dose can be calculated based on weight or BSA:

Based on Weight:

Patient Weight (kg) × Prescribed lopinavir dose (mg/kg) = Administered lopinavir dose (mg)

Based on BSA:

Patient BSA (m^2) × Prescribed lopinavir dose (mg/m^2) = Administered lopinavir dose (mg)

If KALETRA oral solution is used, the volume (mL) of KALETRA solution can be determined as follows:

Volume of KALETRA solution (mL) = Administered lopinavir dose (mg) ÷ 80 (mg/mL)

Oral Solution Dosage Recommendation in Pediatric Patients 14 Days to Less Than 18 Years:

Table 4 summarizes the recommended daily dosing regimen for pediatric patients 14 days to less than 18 years of age using the oral solution.

KALETRA administered in combination with efavirenz, nevirapine, or nelfinavir in patients younger than 6 months of age is not recommended. Total dose of KALETRA oral solution in pediatric patients should not exceed the recommended adult daily dose of 400/100 mg (5mL) twice daily.

Table 4. KALETRA Oral Solution Daily Dosage Recommendations in Pediatric Patients 14 days to Less Than 18 Years Without Concomitant Efavirenz, Nevirapine, or Nelfinavir
Patient Age | Based on Weight (mg/kg) |  | Based on BSA (mg/m^2) | Frequency
14 days to 6 months | 16/4 |  | 300/75 | Given twice daily
Older than 6 months to less than 18 years | Less than15 kg | 12/3 | 230/57.5 | Given twice daily
Older than 6 months to less than 18 years | 15 kg to 40 kg | 10/2.5 | 230/57.5 | Given twice daily

Tablet Dosage Recommendation in Pediatric Patients Older than 6 Months to Less than 18 Years:

Table 5 provides the dosing recommendations for pediatric patients older than 6 months to less than 18 years of age based on body weight or body surface area for KALETRA tablets.

Table 5. KALETRA Tablet Daily Dosage Recommendations in Pediatric Patients > 6 Months to < 18 Years of Age Without Concomitant Efavirenz, Nevirapine, or Nelfinavir
Body Weight (kg) | Body Surface Area (m^2)* | Recommended number of 100/25 mg Tablets Twice Daily
≥15 to 25 | ≥0.6 to < 0.9 | 2
>25 to 35 | ≥0.9 to < 1.4 | 3
>35 | ≥1.4 | 4
* KALETRA oral solution is available for children with a BSA less than 0.6 m^2 or those who are unable to reliably swallow a tablet.

Concomitant Therapy: Efavirenz, Nevirapine, or Nelfinavir

Dosing recommendations using oral solution

Table 6 provides the dosing recommendations for pediatric patients older than 6 months to less than 18 years of age based on body weight or body surface area for KALETRA Oral Solution when given in combination with efavirenz, nevirapine, or nelfinavir:

Table 6. KALETRA Oral Solution Daily Dosage Recommendations for Pediatric Patients > 6 Months to < 18 Years of Age With Concomitant Efavirenz, Nevirapine, or Nelfinavir
Patient Age | Based on Weight (mg/kg) |  | Based on BSA (mg/m^2) | Frequency
> 6 months to < 18 years | <15 kg | 13/3.25 | 300/75 | Given twice daily
> 6 months to < 18 years | ≥15 kg to 45 kg | 11/2.75 | 300/75 | Given twice daily

Dosing recommendations using tablets

Table 7 provides the dosing recommendations for pediatric patients older than 6 months to less than 18 years of age based on body weight or body surface area for KALETRA tablets when given in combination with efavirenz, nevirapine, or nelfinavir.

Table 7. KALETRA Tablet Daily Dosage Recommendations for Pediatric Patients > 6 Months to < 18 Years of Age With Concomitant Efavirenz†, Nevirapine, or Nelfinavir†
Body Weight (kg) | Body Surface Area (m^2)* | Recommended number of 100/25 mg Tablets Twice Daily
≥15 to 20 | ≥0.6 to < 0.8 | 2
>20 to 30 | ≥0.8 to < 1.2 | 3
>30 to 45 | ≥1.2 to <1.7 | 4
>45 | ≥1.7 | 5 [see Dosage and Administration (2.4)]
* KALETRA oral solution is available for children with a BSA less than 0.6 m^2 or those who are unable to reliably swallow a tablet.
† Please refer to the individual product labels for appropriate dosing in children.

2.5 Dosage Recommendations in Pregnancy

Administer 400/100 mg of KALETRA twice daily in pregnant patients with no documented lopinavir-associated resistance substitutions.

- Once daily KALETRA dosing is not recommended in pregnancy [see Use in Specific Populations (8.1) and Clinical Pharmacology (12.3)] .
- There are insufficient data to recommend dosing in pregnant women with any documented lopinavir-associated resistance substitutions.
- No dosage adjustment of KALETRA is required for patients during the postpartum period.
- Avoid use of KALETRA oral solution in pregnant women [see Use in Specific Populations (8.1)] .

3 DOSAGE FORMS AND STRENGTHS

- Tablets:
  - 200 mg lopinavir, 50 mg ritonavir: Yellow, film-coated, ovaloid, debossed with the “a” logo and the code KA containing 200 mg lopinavir and 50 mg ritonavir.
  - 100 mg lopinavir, 25 mg ritonavir: Pale yellow, film-coated, ovaloid, debossed with the “a” logo and the code KC containing 100 mg lopinavir and 25 mg ritonavir.
  - 200 mg lopinavir, 50 mg ritonavir: Red, film-coated, ovaloid, debossed with the “a” logo and the code AL containing 200 mg lopinavir and 50 mg ritonavir.
  - 100 mg lopinavir, 25 mg ritonavir: Pink, film-coated, ovaloid, debossed with the “a” logo and the code AC containing 100 mg lopinavir and 25 mg ritonavir.
- Oral Solution:
  - Light yellow to orange colored liquid containing 400 mg lopinavir and 100 mg ritonavir per 5 mL (80 mg lopinavir and 20 mg ritonavir per mL).

4 CONTRAINDICATIONS

- KALETRA is contraindicated in patients with previously demonstrated clinically significant hypersensitivity (e.g., toxic epidermal necrolysis, Stevens-Johnson syndrome, erythema multiforme, urticaria, angioedema) to any of its ingredients, including ritonavir.

- KALETRA is contraindicated with drugs that are highly dependent on CYP3A for clearance and for which elevated plasma concentrations are associated with serious and/or life-threatening reactions [see Drug Interactions (7.1) and Clinical Pharmacology (12.3)] .
  - Alpha 1- Adrenoreceptor Antagonist: alfuzosin
  - Antianginal: ranolazine
  - Antiarrhythmic: dronedarone
  - Anti-gout: colchicine
  - Antipsychotics: lurasidone, pimozide
  - Ergot Derivatives: dihydroergotamine, ergotamine, methylergonovine
  - GI Motility Agent: cisapride
  - Hepatitis C direct acting antiviral: elbasvir/grazoprevir
  - HMG-CoA Reductase Inhibitors: lovastatin, simvastatin
  - Microsomal triglyceride transfer protein (MTTP) Inhibitor: lomitapideMicrosomal triglyceride transfer protein (MTTP) Inhibitor: lomitapide
  - PDE5 Inhibitor: sildenafil (Revatio®) when used for the treatment of pulmonary arterial hypertension
  - Sedative/Hypnotics: triazolam, orally administered midazolam
- KALETRA is contraindicated with drugs that are potent CYP3A inducers where significantly reduced lopinavir plasma concentrations may be associated with the potential for loss of virologic response and possible resistance and cross-resistance [see Drug Interactions (7.2) and Clinical Pharmacology (12.3)] .
  - Anticancer Agents: apalutamide
  - Antimycobacterial: rifampin
  - Herbal Products: St. John's Wort (hypericum perforatum)

5 WARNINGS AND PRECAUTIONS

5.1 Risk of Serious Adverse Reactions Due to Drug Interactions

Initiation of KALETRA, a CYP3A inhibitor, in patients receiving medications metabolized by CYP3A or initiation of medications metabolized by CYP3A in patients already receiving KALETRA, may increase plasma concentrations of medications metabolized by CYP3A. Initiation of medications that inhibit or induce CYP3A may increase or decrease concentrations of KALETRA, respectively. These interactions may lead to:

- Clinically significant adverse reactions, potentially leading to severe, life-threatening, or fatal events from greater exposures of concomitant medications.
- Clinically significant adverse reactions from greater exposures of KALETRA.
- Loss of therapeutic effect of KALETRA and possible development of resistance.

See Table 12 for steps to prevent or manage these possible and known significant drug interactions, including dosing recommendations [see Drug Interactions (7)] . Consider the potential for drug interactions prior to and during KALETRA therapy; review concomitant medications during KALETRA therapy, and monitor for the adverse reactions associated with the concomitant medications [see Contraindications (4) and Drug Interactions (7)] .

5.2 Toxicity in Preterm Neonates

KALETRA oral solution contains the excipients ethanol, approximately 42% (v/v) and propylene glycol, approximately 15% (w/v). When administered concomitantly with propylene glycol, ethanol competitively inhibits the metabolism of propylene glycol, which may lead to elevated concentrations. Preterm neonates may be at increased risk of propylene glycol-associated adverse events due to diminished ability to metabolize propylene glycol, thereby leading to accumulation and potential adverse events. Postmarketing life-threatening cases of cardiac toxicity (including complete AV block, bradycardia, and cardiomyopathy), lactic acidosis, acute renal failure, CNS depression and respiratory complications leading to death have been reported, predominantly in preterm neonates receiving KALETRA oral solution.

KALETRA oral solution should not be used in preterm neonates in the immediate postnatal period because of possible toxicities. A safe and effective dose of KALETRA oral solution in this patient population has not been established. However, if the benefit of using KALETRA oral solution to treat HIV infection in infants immediately after birth outweighs the potential risks, infants should be monitored closely for increases in serum osmolality and serum creatinine, and for toxicity related to KALETRA oral solution including: hyperosmolality, with or without lactic acidosis, renal toxicity, CNS depression (including stupor, coma, and apnea), seizures, hypotonia, cardiac arrhythmias and ECG changes, and hemolysis. Total amounts of ethanol and propylene glycol from all medicines that are to be given to infants should be taken into account in order to avoid toxicity from these excipients [see Dosage and Administration (2.4) and Overdosage (10)] .

5.3 Pancreatitis

Pancreatitis has been observed in patients receiving KALETRA therapy, including those who developed marked triglyceride elevations. In some cases, fatalities have been observed. Although a causal relationship to KALETRA has not been established, marked triglyceride elevations are a risk factor for development of pancreatitis [see Warnings and Precautions (5.9)] . Patients with advanced HIV-1 disease may be at increased risk of elevated triglycerides and pancreatitis, and patients with a history of pancreatitis may be at increased risk for recurrence during KALETRA therapy.

Pancreatitis should be considered if clinical symptoms (nausea, vomiting, abdominal pain) or abnormalities in laboratory values (such as increased serum lipase or amylase values) suggestive of pancreatitis occur. Patients who exhibit these signs or symptoms should be evaluated and KALETRA and/or other antiretroviral therapy should be suspended as clinically appropriate.

5.4 Hepatotoxicity

Patients with underlying hepatitis B or C or marked elevations in transaminase prior to treatment may be at increased risk for developing or worsening of transaminase elevations or hepatic decompensation with use of KALETRA.

There have been postmarketing reports of hepatic dysfunction, including some fatalities. These have generally occurred in patients with advanced HIV-1 disease taking multiple concomitant medications in the setting of underlying chronic hepatitis or cirrhosis. A causal relationship with KALETRA therapy has not been established.

Elevated transaminases with or without elevated bilirubin levels have been reported in HIV-1 mono-infected and uninfected patients as early as 7 days after the initiation of KALETRA in conjunction with other antiretroviral agents. In some cases, the hepatic dysfunction was serious; however, a definitive causal relationship with KALETRA therapy has not been established.

Appropriate laboratory testing should be conducted prior to initiating therapy with KALETRA and patients should be monitored closely during treatment. Increased AST/ALT monitoring should be considered in the patients with underlying chronic hepatitis or cirrhosis, especially during the first several months of KALETRA treatment [see Use in Specific Populations (8.6)].

5.5 QT Interval Prolongation

Postmarketing cases of QT interval prolongation and torsade de pointes have been reported although causality of KALETRA could not be established. Avoid use in patients with congenital long QT syndrome, those with hypokalemia, and with other drugs that prolong the QT interval [see Clinical Pharmacology (12.3)] .

5.6 PR Interval Prolongation

Lopinavir/ritonavir prolongs the PR interval in some patients. Cases of second or third degree atrioventricular block have been reported. KALETRA should be used with caution in patients with underlying structural heart disease, pre-existing conduction system abnormalities, ischemic heart disease or cardiomyopathies, as these patients may be at increased risk for developing cardiac conduction abnormalities.

The impact on the PR interval of co-administration of KALETRA with other drugs that prolong the PR interval (including calcium channel blockers, beta-adrenergic blockers, digoxin and atazanavir) has not been evaluated. As a result, co-administration of KALETRA with these drugs should be undertaken with caution, particularly with those drugs metabolized by CYP3A. Clinical monitoring is recommended [see Clinical Pharmacology (12.3)] .

5.7 Diabetes Mellitus/Hyperglycemia

New onset diabetes mellitus, exacerbation of pre-existing diabetes mellitus, and hyperglycemia have been reported during post-marketing surveillance in HIV-1 infected patients receiving protease inhibitor therapy. Some patients required either initiation or dose adjustments of insulin or oral hypoglycemic agents for treatment of these events. In some cases, diabetic ketoacidosis has occurred. In those patients who discontinued protease inhibitor therapy, hyperglycemia persisted in some cases. Because these events have been reported voluntarily during clinical practice, estimates of frequency cannot be made and a causal relationship between protease inhibitor therapy and these events has not been established. Consider monitoring for hyperglycemia, new onset diabetes mellitus or an exacerbation of diabetes mellitus in patients treated with KALETRA.

5.8 Immune Reconstitution Syndrome

Immune reconstitution syndrome has been reported in patients treated with combination antiretroviral therapy, including KALETRA. During the initial phase of combination antiretroviral treatment, patients whose immune system responds may develop an inflammatory response to indolent or residual opportunistic infections (such as Mycobacterium avium infection, cytomegalovirus, Pneumocystis jirovecii pneumonia [PCP], or tuberculosis) which may necessitate further evaluation and treatment.

Autoimmune disorders (such as Graves’ disease, polymyositis, and Guillain-Barré syndrome) have also been reported to occur in the setting of immune reconstitution, however, the time to onset is more variable, and can occur many months after initiation of treatment.

5.9 Lipid Elevations

Treatment with KALETRA has resulted in large increases in the concentration of total cholesterol and triglycerides [see Adverse Reactions (6.1)] . Triglyceride and cholesterol testing should be performed prior to initiating KALETRA therapy and at periodic intervals during therapy. Lipid disorders should be managed as clinically appropriate, taking into account any potential drug-drug interactions with KALETRA and HMG-CoA reductase inhibitors [see Contraindications (4) and Drug Interactions (7.3)] .

5.10 Fat Redistribution

Redistribution/accumulation of body fat including central obesity, dorsocervical fat enlargement (buffalo hump), peripheral wasting, facial wasting, breast enlargement, and "cushingoid appearance" have been observed in patients receiving antiretroviral therapy. The mechanism and long-term consequences of these events are currently unknown. A causal relationship has not been established.

5.11 Patients with Hemophilia

Increased bleeding, including spontaneous skin hematomas and hemarthrosis have been reported in patients with hemophilia type A and B treated with protease inhibitors. In some patients additional factor VIII was given. In more than half of the reported cases, treatment with protease inhibitors was continued or reintroduced. A causal relationship between protease inhibitor therapy and these events has not been established.

5.12 Resistance/Cross-resistance

Because the potential for HIV cross-resistance among protease inhibitors has not been fully explored in KALETRA-treated patients, it is unknown what effect therapy with KALETRA will have on the activity of subsequently administered protease inhibitors [see Microbiology (12.4)].

6 ADVERSE REACTIONS

The following adverse reactions are discussed in greater detail in other sections of the labeling.

- QT Interval Prolongation, PR Interval Prolongation [see Warnings and Precautions (5.5, 5.6)]
- Drug Interactions [see Warnings and Precautions (5.1)]
- Pancreatitis [see Warnings and Precautions (5.3)]
- Hepatotoxicity [see Warnings and Precautions (5.4)]

6.1 Clinical Trials Experience

Because clinical trials are conducted under widely varying conditions, adverse reactions rates observed in the clinical trials of a drug cannot be directly compared to rates in the clinical trials of another drug and may not reflect the rates observed in clinical practice.

Adverse Reactions in Adults

The safety of KALETRA has been investigated in about 2,600 patients in Phase II-IV clinical trials, of which about 700 have received a dose of 800/200 mg (6 capsules or 4 tablets) once daily. Along with nucleoside reverse transcriptase inhibitors (NRTIs), in some studies, KALETRA was used in combination with efavirenz or nevirapine.

In clinical studies the incidence of diarrhea in patients treated with either KALETRA capsules or tablets was greater in those patients treated once daily than in those patients treated twice daily. Any grade of diarrhea was reported by at least half of patients taking once daily Kaletra capsules or tablets. At the time of treatment discontinuation, 4.2-6.3% of patients taking once daily Kaletra and 1.8-3.7% of those taking twice daily Kaletra reported ongoing diarrhea.

Commonly reported adverse reactions to KALETRA included diarrhea, nausea, vomiting, hypertriglyceridemia and hypercholesterolemia. Diarrhea, nausea and vomiting may occur at the beginning of the treatment while hypertriglyceridemia and hypercholesterolemia may occur later. The following have been identified as adverse reactions of moderate or severe intensity (Table 8):

Table 8. Adverse Reactions of Moderate or Severe Intensity Occurring in at Least 0.1% of Adult Patients Receiving KALETRA in Combined Phase II/IV Studies (N=2,612)
System Organ Class (SOC) and Adverse Reaction |  | n | %
BLOOD AND LYMPHATIC SYSTEM DISORDERS
anemia* |  | 54 | 2.1
leukopenia and neutropenia* |  | 44 | 1.7
lymphadenopathy* |  | 35 | 1.3
CARDIAC DISORDERS
atherosclerosis such as myocardial infarction* |  | 10 | 0.4
atrioventricular block* |  | 3 | 0.1
tricuspid valve incompetence* |  | 3 | 0.1
EAR AND LABYRINTH DISORDERS
vertigo* |  | 7 | 0.3
tinnitus |  | 6 | 0.2
ENDOCRINE DISORDERS
hypogonadism* |  | 16 | 0.8^1
EYE DISORDERS
visual impairment* |  | 8 | 0.3
GASTROINTESTINAL DISORDERS
diarrhea* |  | 510 | 19.5
nausea |  | 269 | 10.3
vomiting* |  | 177 | 6.8
abdominal pain (upper and lower)* |  | 160 | 6.1
gastroenteritis and colitis* |  | 66 | 2.5
dyspepsia |  | 53 | 2.0
pancreatitis* |  | 45 | 1.7
Gastroesophageal Reflux Disease (GERD)* |  | 40 | 1.5
hemorrhoids |  | 39 | 1.5
flatulence |  | 36 | 1.4
abdominal distension |  | 34 | 1.3
constipation* |  | 26 | 1.0
stomatitis and oral ulcers* |  | 24 | 0.9
duodenitis and gastritis* |  | 20 | 0.8
gastrointestinal hemorrhage including rectal hemorrhage* |  | 13 | 0.5
dry mouth |  | 9 | 0.3
gastrointestinal ulcer* |  | 6 | 0.2
fecal incontinence |  | 5 | 0.2
GENERAL DISORDERS AND ADMINISTRATION SITE CONDITIONS
fatigue including asthenia* |  | 198 | 7.6
HEPATOBILIARY DISORDERS
hepatitis including AST, ALT, and GGT increases* |  | 91 | 3.5
hepatomegaly |  | 5 | 0.2
cholangitis |  | 3 | 0.1
hepatic steatosis |  | 3 | 0.1
IMMUNE SYSTEM DISORDERS
hypersensitivity including urticaria and angioedema* |  | 70 | 2.7
immune reconstitution syndrome |  | 3 | 0.1
INFECTIONS AND INFESTATIONS
upper respiratory tract infection* |  | 363 | 13.9
lower respiratory tract infection* |  | 202 | 7.7
skin infections including cellulitis, folliculitis, and furuncle* |  | 86 | 3.3
METABOLISM AND NUTRITION DISORDERS
hypercholesterolemia* |  | 192 | 7.4
hypertriglyceridemia* |  | 161 | 6.2
weight decreased* |  | 61 | 2.3
decreased appetite |  | 52 | 2.0
blood glucose disorders including diabetes mellitus* |  | 30 | 1.1
weight increased* |  | 20 | 0.8
lactic acidosis* |  | 11 | 0.4
increased appetite |  | 5 | 0.2
MUSCULOSKELETAL AND CONNECTIVE TISSUE DISORDERS
musculoskeletal pain including arthralgia and back pain* |  | 166 | 6.4
myalgia* |  | 46 | 1.8
muscle disorders such as weakness and spasms* |  | 34 | 1.3
rhabdomyolysis* |  | 18 | 0.7
osteonecrosis |  | 3 | 0.1
NERVOUS SYSTEM DISORDERS
headache including migraine* |  | 165 | 6.3
insomnia* |  | 99 | 3.8
neuropathy and peripheral neuropathy* |  | 51 | 2.0
dizziness* |  | 45 | 1.7
ageusia* |  | 19 | 0.7
convulsion* |  | 9 | 0.3
tremor* |  | 9 | 0.3
cerebral vascular event* |  | 6 | 0.2
PSYCHIATRIC DISORDERS
anxiety* |  | 101 | 3.9
abnormal dreams* |  | 19 | 0.7
libido decreased |  | 19 | 0.7
RENAL AND URINARY DISORDERS
renal failure* |  | 31 | 1.2
hematuria* |  | 20 | 0.8
nephritis* |  | 3 | 0.1
REPRODUCTIVE SYSTEM AND BREAST DISORDERS
erectile dysfunction* |  | 34 | 1.7^1
menstrual disorders - amenorrhea, menorrhagia* |  | 10 | 1.7^2
SKIN AND SUBCUTANEOUS TISSUE DISORDERS
rash including maculopapular rash* |  | 99 | 3.8
lipodystrophy acquired including facial wasting* |  | 58 | 2.2
dermatitis/rash including eczema and seborrheic dermatitis* |  | 50 | 1.9
night sweats* |  | 42 | 1.6
pruritus* |  | 29 | 1.1
alopecia |  | 10 | 0.4
capillaritis and vasculitis* |  | 3 | 0.1
VASCULAR DISORDERS
hypertension* |  | 47 | 1.8
deep vein thrombosis* |  | 17 | 0.7
*Represents a medical concept including several similar MedDRA PTs
^1. Percentage of male population (N=2,038)
^2. Percentage of female population (N=574)

Laboratory Abnormalities in Adults

The percentages of adult patients treated with combination therapy with Grade 3-4 laboratory abnormalities are presented in Table 9 (treatment-naïve patients) and Table 10 (treatment-experienced patients).

Table 9. Grade 3-4 Laboratory Abnormalities Reported in ≥ 2% of Adult Antiretroviral-Naïve Patients
 |  | Study 863 (48 Weeks) |  | Study 720 (360 Weeks) | Study 730 (48 Weeks)
Variable | Limit^1 | KALETRA 400/100 mg Twice Daily + d4T +3TC (N = 326) | Nelfinavir 750 mg Three Times Daily + d4T + 3TC (N = 327) | KALETRA Twice Daily + d4T + 3TC (N = 100) | KALETRA Once Daily + TDF +FTC (N=333) | KALETRA Twice Daily + TDF +FTC (N=331)
Chemistry | High
Glucose | > 250 mg/dL | 2% | 2% | 4% | 0% | <1%
Uric Acid | > 12 mg/dL | 2% | 2% | 5% | <1% | 1%
SGOT/ AST^2 | > 180 U/L | 2% | 4% | 10% | 1% | 2%
SGPT/ ALT^2 | >215 U/L | 4% | 4% | 11% | 1% | 1%
GGT | >300 U/L | N/A | N/A | 10% | N/A | N/A
Total Cholesterol | >300 mg/dL | 9% | 5% | 27% | 4% | 3%
Triglycerides | >750 mg/dL | 9% | 1% | 29% | 3% | 6%
Amylase | >2 x ULN | 3% | 2% | 4% | N/A | N/A
Lipase | >2 x ULN | N/A | N/A | N/A | 3% | 5%
Chemistry | Low
Calculated Creatinine Clearance | <50 mL/min | N/A | N/A | N/A | 2% | 2%
Hematology | Low
Neutrophils | <0.75 x 10^9/L | 1% | 3% | 5% | 2% | 1%
1 ULN = upper limit of the normal range; N/A = Not Applicable.
2 Criterion for Study 730 was >5x ULN (AST/ALT).

Table 10. Grade 3-4 Laboratory Abnormalities Reported in ≥ 2% of Adult Protease Inhibitor-Experienced Patients
 |  | Study 888 (48 Weeks) |  | Study 957^2 and Study 765^3 (84-144 Weeks) | Study 802 (48 Weeks)
Variable | Limit^1 | KALETRA 400/100 mg Twice Daily + NVP + NRTIs (N = 148) | Investigator-Selected Protease Inhibitor(s) + NVP + NRTIs (N = 140) | KALETRA Twice Daily + NNRTI + NRTIs (N = 127) | KALETRA 800/200 mg Once Daily +NRTIs (N=300) | KALETRA 400/100 mg Twice Daily +NRTIs (N=299)
Chemistry | High
Glucose | >250 mg/dL | 1% | 2% | 5% | 2% | 2%
Total Bilirubin | >3.48 mg/dL | 1% | 3% | 1% | 1% | 1%
SGOT/AST^4 | >180 U/L | 5% | 11% | 8% | 3% | 2%
SGPT/ALT^4 | >215 U/L | 6% | 13% | 10% | 2% | 2%
GGT | >300 U/L | N/A | N/A | 29% | N/A | N/A
Total Cholesterol | >300 mg/dL | 20% | 21% | 39% | 6% | 7%
Triglycerides | >750 mg/dL | 25% | 21% | 36% | 5% | 6%
Amylase | >2 x ULN | 4% | 8% | 8% | 4% | 4%
Lipase | >2 x ULN | N/A | N/A | N/A | 4% | 1%
Creatine Phosphokinase | >4 x ULN | N/A | N/A | N/A | 4% | 5%
Chemistry | Low
Calculated Creatinine Clearance | <50 mL/min | N/A | N/A | N/A | 3% | 3%
Inorganic Phosphorus | <1.5 mg/dL | 1% | 0% | 2% | 1% | <1%
Hematology | Low
Neutrophils | <0.75 x 10^9/L | 1% | 2% | 4% | 3% | 4%
Hemoglobin | <80 g/L | 1% | 1% | 1% | 1% | 2%
1 ULN = upper limit of the normal range; N/A = Not Applicable.
2 Includes clinical laboratory data from patients receiving 400/100 mg twice daily (n = 29) or 533/133 mg twice daily (n = 28) for 84 weeks. Patients received KALETRA in combination with NRTIs and efavirenz.
3 Includes clinical laboratory data from patients receiving 400/100 mg twice daily (n = 36) or 400/200 mg twice daily (n = 34) for 144 weeks. Patients received KALETRA in combination with NRTIs and nevirapine.
4 Criterion for Study 802 was >5x ULN (AST/ALT).

Adverse Reactions in Pediatric Patients

KALETRA oral solution dosed up to 300/75 mg/m^2 has been studied in 100 pediatric patients 6 months to 12 years of age. The adverse reaction profile seen during Study 940 was similar to that for adult patients.

Dysgeusia (22%), vomiting (21%), and diarrhea (12%) were the most common adverse reactions of any severity reported in pediatric patients treated with combination therapy for up to 48 weeks in Study 940. A total of 8 patients experienced adverse reactions of moderate to severe intensity. The adverse reactions meeting these criteria and reported for the 8 subjects include: hypersensitivity (characterized by fever, rash and jaundice), pyrexia, viral infection, constipation, hepatomegaly, pancreatitis, vomiting, alanine aminotransferase increased, dry skin, rash, and dysgeusia. Rash was the only event of those listed that occurred in 2 or more subjects (N = 3).

KALETRA oral solution dosed at 300/75 mg/m^2 has been studied in 31 pediatric patients 14 days to 6 months of age. The adverse reaction profile in Study 1030 was similar to that observed in older children and adults. No adverse reaction was reported in greater than 10% of subjects. Adverse drug reactions of moderate to severe intensity occurring in 2 or more subjects included decreased neutrophil count (N=3), anemia (N=2), high potassium (N=2), and low sodium (N=2).

KALETRA oral solution and soft gelatin capsules dosed at higher than recommended doses including 400/100 mg/m^2 (without concomitant NNRTI) and 480/120 mg/m^2 (with concomitant NNRTI) have been studied in 26 pediatric patients 7 to 18 years of age in Study 1038. Patients also had saquinavir mesylate added to their regimen at Week 4. Rash (12%), blood cholesterol abnormal (12%) and blood triglycerides abnormal (12%) were the only adverse reactions reported in greater than 10% of subjects. Adverse drug reactions of moderate to severe intensity occurring in 2 or more subjects included rash (N=3), blood triglycerides abnormal (N=3), and electrocardiogram QT prolonged (N=2). Both subjects with QT prolongation had additional predisposing conditions such as electrolyte abnormalities, concomitant medications, or pre-existing cardiac abnormalities.

Laboratory Abnormalities in Pediatric Patients

The percentages of pediatric patients treated with combination therapy including KALETRA with Grade 3-4 laboratory abnormalities are presented in Table 11.

Table 11. Grade 3-4 Laboratory Abnormalities Reported in ≥ 2% Pediatric Patients in Study 940
Variable | Limit^1 | KALETRA Twice Daily + RTIs (N = 100)
Chemistry | High
Sodium | > 149 mEq/L | 3%
Total Bilirubin | ≥ 3.0 x ULN | 3%
SGOT/AST | > 180 U/L | 8%
SGPT/ALT | > 215 U/L | 7%
Total Cholesterol | > 300 mg/dL | 3%
Amylase | > 2.5 x ULN | 7%^2
Chemistry | Low
Sodium | < 130 mEq/L | 3%
Hematology | Low
Platelet Count | < 50 x 10^9/L | 4%
Neutrophils | < 0.40 x 10^9/L | 2%
1 ULN = upper limit of the normal range.
2 Subjects with Grade 3-4 amylase confirmed by elevations in pancreatic amylase.

6.2 Postmarketing Experience

The following adverse reactions have been reported during postmarketing use of KALETRA. Because these reactions are reported voluntarily from a population of unknown size, it is not possible to reliably estimate their frequency or establish a causal relationship to KALETRA exposure.

Body as a Whole
Redistribution/accumulation of body fat has been reported [see Warnings and Precautions (5.10)] .

Cardiovascular
Bradyarrhythmias. First-degree AV block, second-degree AV block, third-degree AV block, QTc interval prolongation, torsades (torsade) de pointes [see Warnings and Precautions (5.5, 5.6)] .

Renal and Urinary Disorders
Nephrolithiasis

Skin and Appendages
Toxic epidermal necrolysis (TEN), Stevens-Johnson syndrome and erythema multiforme.

7 DRUG INTERACTIONS

7.1 Potential for KALETRA to Affect Other Drugs

Lopinavir/ritonavir is an inhibitor of CYP3A and may increase plasma concentrations of agents that are primarily metabolized by CYP3A. Agents that are extensively metabolized by CYP3A and have high first pass metabolism appear to be the most susceptible to large increases in AUC (> 3-fold) when co-administered with KALETRA. Thus, co-administration of KALETRA with drugs highly dependent on CYP3A for clearance and for which elevated plasma concentrations are associated with serious and/or life-threatening events is contraindicated. Co-administration with other CYP3A substrates may require a dose adjustment or additional monitoring as shown in Table 12.

Additionally, KALETRA induces glucuronidation.

Published data suggest that lopinavir is an inhibitor of OATP1B1.

These examples are a guide and not considered a comprehensive list of all possible drugs that may interact with lopinavir/ritonavir. The healthcare provider should consult appropriate references for comprehensive information.

7.2 Potential for Other Drugs to Affect Lopinavir

Lopinavir/ritonavir is a CYP3A substrate; therefore, drugs that induce CYP3A may decrease lopinavir plasma concentrations and reduce KALETRA’s therapeutic effect. Although not observed in the KALETRA/ketoconazole drug interaction study, co-administration of KALETRA and other drugs that inhibit CYP3A may increase lopinavir plasma concentrations.

7.3 Established and Other Potentially Significant Drug Interactions

Table 12 provides a listing of established or potentially clinically significant drug interactions. Alteration in dose or regimen may be recommended based on drug interaction studies or predicted interaction [see Contraindications (4), Warnings and Precautions (5.1), Clinical Pharmacology (12.3)] for magnitude of interaction.

Table 12. Established and Other Potentially Significant Drug Interactions
Concomitant Drug Class: Drug Name | Effect on Concentration of Lopinavir or Concomitant Drug | Clinical Comments
HIV-1 Antiviral Agents
HIV-1 Protease Inhibitor: fosamprenavir/ritonavir | ↓ amprenavir ↓ lopinavir | An increased rate of adverse reactions has been observed with co-administration of these medications. Appropriate doses of the combinations with respect to safety and efficacy have not been established.
HIV-1 Protease Inhibitor: indinavir* | ↑ indinavir | Decrease indinavir dose to 600 mg twice daily, when co-administered with KALETRA 400/100 mg twice daily. KALETRA once daily has not been studied in combination with indinavir.
HIV-1 Protease Inhibitor: nelfinavir* | ↑ nelfinavir ↑ M8 metabolite of nelfinavir ↓ lopinavir | KALETRA once daily in combination with nelfinavir is not recommended [see Dosage and Administration (2)] .
HIV-1 Protease Inhibitor: ritonavir* | ↑ lopinavir | Appropriate doses of additional ritonavir in combination with KALETRA with respect to safety and efficacy have not been established.
HIV-1 Protease Inhibitor: saquinavir | ↑ saquinavir | The saquinavir dose is 1000 mg twice daily, when co-administered with KALETRA 400/100 mg twice daily. KALETRA once daily has not been studied in combination with saquinavir.
HIV-1 Protease Inhibitor: tipranavir* | ↓ lopinavir | Co-administration with tipranavir (500 mg twice daily) and ritonavir (200 mg twice daily) is not recommended.
HIV CCR5 – Antagonist: maraviroc* | ↑ maraviroc | When co-administered, patients should receive 150 mg twice daily of maraviroc. For further details see complete prescribing information for maraviroc.
Non-nucleoside Reverse Transcriptase Inhibitors: efavirenz*, nevirapine* | ↓ lopinavir | Increase the dose of KALETRA tablets to 500/125 mg when KALETRA tablet is co-administered with efavirenz or nevirapine. KALETRA once daily in combination with efavirenz or nevirapine is not recommended [see Dosage and Administration (2)] .
Non-nucleoside Reverse Transcriptase Inhibitor: delavirdine | ↑ lopinavir | Appropriate doses of the combination with respect to safety and efficacy have not been established.
Nucleoside Reverse Transcriptase Inhibitor: didanosine |  | KALETRA tablets can be administered simultaneously with didanosine without food. For KALETRA oral solution, it is recommended that didanosine be administered on an empty stomach; therefore, didanosine should be given one hour before or two hours after KALETRA oral solution (given with food).
Nucleoside Reverse Transcriptase Inhibitor: tenofovir disoproxil fumarate* | ↑ tenofovir | Patients receiving KALETRA and tenofovir should be monitored for adverse reactions associated with tenofovir.
Nucleoside Reverse Transcriptase Inhibitors: abacavir zidovudine | ↓ abacavir ↓ zidovudine | The clinical significance of this potential interaction is unknown.
Other Agents
Alpha 1- Adrenoreceptor Antagonist: alfuzosin | ↑ alfuzosin | Contraindicated due to potential hypotension [see Contraindications (4)] .
Antianginal: ranolazine | ↑ ranolazine | Contraindicated due to potential for serious and/or life-threatening reactions [see Contraindications (4)] .
Antiarrhythmics: dronedarone | ↑ dronedarone | Contraindicated due to potential for cardiac arrhythmias [see Contraindications (4)] .
Antiarrhythmics e.g. amiodarone, bepridil, lidocaine (systemic), quinidine | ↑ antiarrhythmics | Caution is warranted and therapeutic concentration monitoring (if available) is recommended for antiarrhythmics when co-administered with KALETRA.
Anticancer Agents: abemaciclib, apalutamide, encorafenib, ibrutinib, ivosidenib, dasatinib, neratinib, nilotinib, venetoclax, vinblastine, vincristine | ↑ anticancer agents ↓lopinavir/ritonavir# | Apalutamide is contraindicated due to potential for loss of virologic response and possible resistance to KALETRA or to the class of protease inhibitors [see Contraindications (4)] . Avoid co-administration of encorafenib or ivosidenib with KALETRA due to potential risk of serious adverse events such as QT interval prolongation. If co-administration of encorafenib with KALETRA cannot be avoided, modify dose as recommended in encorafenib USPI. If co-administration of ivosidenib with KALETRA cannot be avoided, reduce ivosidenib dose to 250 mg once daily. Avoid use of neratinib, venetoclax or ibrutinib with KALETRA. For vincristine and vinblastine, consideration should be given to temporarily withholding the ritonavir-containing antiretroviral regimen in patients who develop significant hematologic or gastrointestinal side effects when KALETRA is administered concurrently with vincristine or vinblastine. If the antiretroviral regimen must be withheld for a prolonged period, consideration should be given to initiating a revised regimen that does not include a CYP3A or P-gp inhibitor. A decrease in the dosage or an adjustment of the dosing interval of nilotinib and dasatinib may be necessary for patients requiring co-administration with strong CYP3A inhibitors such as KALETRA. Please refer to the nilotinib and dasatinib prescribing information for dosing instructions.
Anticoagulants: warfarin, rivaroxaban | ↑↓ warfarin ↑ rivaroxaban | Concentrations of warfarin may be affected. Initial frequent monitoring of the INR during KALETRA and warfarin co-administration is recommended. Avoid concomitant use of rivaroxaban and KALETRA. Co-administration of KALETRA and rivaroxaban may lead to increased risk of bleeding.
Anticonvulsants: carbamazepine, phenobarbital, phenytoin | ↓ lopinavir ↓ phenytoin | KALETRA may be less effective due to decreased lopinavir plasma concentrations in patients taking these agents concomitantly and should be used with caution. KALETRA once daily in combination with carbamazepine, phenobarbital, or phenytoin is not recommended. In addition, co-administration of phenytoin and KALETRA may cause decreases in steady-state phenytoin concentrations. Phenytoin levels should be monitored when co-administering with KALETRA.
Anticonvulsants: lamotrigine, valproate | ↓ lamotrigine ↓ or ↔ valproate | A dose increase of lamotrigine or valproate may be needed when co-administered with KALETRA and therapeutic concentration monitoring for lamotrigine may be indicated; particularly during dosage adjustments.
Antidepressant: bupropion | ↓ bupropion ↓ active metabolite, hydroxybupropion | Patients receiving KALETRA and bupropion concurrently should be monitored for an adequate clinical response to bupropion.
Antidepressant: trazodone | ↑ trazodone | Adverse reactions of nausea, dizziness, hypotension and syncope have been observed following co-administration of trazodone and ritonavir. A lower dose of trazodone should be considered.
Anti-infective: clarithromycin | ↑ clarithromycin | For patients with renal impairment, adjust clarithromycin dose as follows:; - For patients on KALETRA with CLCR 30 to 60 mL/min the dose of clarithromycin should be reduced by 50%. - For patients on KALETRA with CLCR < 30 mL/min the dose of clarithromycin should be decreased by 75%.; No dose adjustment for patients with normal renal function is necessary.
Antifungals: ketoconazole*, itraconazole, voriconazole isavuconazonium sulfate* | ↑ ketoconazole ↑ itraconazole ↓ voriconazole ↑ isavuconazonium | High doses of ketoconazole (>200 mg/day) or itraconazole (> 200 mg/day) are not recommended. The coadministration of voriconazole and KALETRA should be avoided unless an assessment of the benefit/risk to the patient justifies the use of voriconazole. Isavuconazonium and Kaletra should be coadministered with caution. Alternative antifungal therapies should be considered in these patients.
Anti-gout: colchicine | ↑ colchicine | Contraindicated due to potential for serious and/or life-threatening reactions in patients with renal and/or hepatic impairment [see Contraindications (4)] . For patients with normal renal or hepatic function: Treatment of gout flares-co-administration of colchicine in patients on KALETRA: 0.6 mg (1 tablet) x 1 dose, followed by 0.3 mg (half tablet) 1 hour later. Dose to be repeated no earlier than 3 days. Prophylaxis of gout flares-co-administration of colchicine in patients on KALETRA: If the original colchicine regimen was 0.6 mg twice a day, the regimen should be adjusted to 0.3 mg once a day. If the original colchicine regimen was 0.6 mg once a day, the regimen should be adjusted to 0.3 mg once every other day. Treatment of familial Mediterranean fever (FMF)-co-administration of colchicine in patients on KALETRA: Maximum daily dose of 0.6 mg (may be given as 0.3 mg twice a day).
Antimycobacterial: rifampin | ↓ lopinavir | Contraindicated due to potential loss of virologic response and possible resistance to KALETRA or to the class of protease inhibitors or other co-administered antiretroviral agents [see Contraindications (4)] .
Antimycobacterial: bedaquiline | ↑ bedaquiline | Bedaquiline should only be used with KALETRA if the benefit of co-administration outweighs the risk.
Antimycobacterial: rifabutin* | ↑ rifabutin and rifabutin metabolite | Dosage reduction of rifabutin by at least 75% of the usual dose of 300 mg/day is recommended (i.e., a maximum dose of 150 mg every other day or three times per week). Increased monitoring for adverse reactions is warranted in patients receiving the combination. Further dosage reduction of rifabutin may be necessary.
Antiparasitic: atovaquone | ↓ atovaquone | Clinical significance is unknown; however, increase in atovaquone doses may be needed.
Antipsychotics: lurasidone pimozide | ↑ lurasidone ↑ pimozide | Contraindicated due to potential for serious and/or life-threatening reactions [see Contraindications (4)] . Contraindicated due to potential for serious and/or life-threatening reactions such as cardiac arrhythmias [see Contraindications (4)] .
Antipsychotics: quetiapine | ↑ quetiapine | Initiation of KALETRA in patients taking quetiapine: Consider alternative antiretroviral therapy to avoid increases in quetiapine exposures. If coadministration is necessary, reduce the quetiapine dose to 1/6 of the current dose and monitor for quetiapine-associated adverse reactions. Refer to the quetiapine prescribing information for recommendations on adverse reaction monitoring. Initiation of quetiapine in patients taking KALETRA: Refer to the quetiapine prescribing information for initial dosing and titration of quetiapine.
Contraceptive: ethinyl estradiol* | ↓ ethinyl estradiol | Because contraceptive steroid concentrations may be altered when KALETRA is co-administered with oral contraceptives or with the contraceptive patch, alternative methods of nonhormonal contraception are recommended.
Dihydropyridine Calcium Channel Blockers: e.g. felodipine, nifedipine, nicardipine | ↑ dihydropyridine calcium channel blockers | Clinical monitoring of patients is recommended and a dose reduction of the dihydropyridine calcium channel blocker may be considered.
Disulfiram/metronidazole |  | KALETRA oral solution contains ethanol, which can produce disulfiram-like reactions when co-administered with disulfiram or other drugs that produce this reaction (e.g., metronidazole).
Endothelin Receptor Antagonists: bosentan | ↑ bosentan | Co-administration of bosentan in patients on KALETRA: In patients who have been receiving KALETRA for at least 10 days, start bosentan at 62.5 mg once daily or every other day based upon individual tolerability. Co-administration of KALETRA in patients on bosentan: Discontinue use of bosentan at least 36 hours prior to initiation of KALETRA. After at least 10 days following the initiation of KALETRA, resume bosentan at 62.5 mg once daily or every other day based upon individual tolerability.
Ergot Derivatives: dihydroergotamine, ergotamine, methylergonovine | ↑ ergot derivatives | Contraindicated due to potential for acute ergot toxicity characterized by peripheral vasospasm and ischemia of the extremities and other tissues [see Contraindications (4)] .
GI Motility Agent: cisapride | ↑ cisapride | Contraindicated due to potential for cardiac arrhythmias [see Contraindications (4)] .
GnRH Receptor Antagonists: elagolix | ↑ elagolix ↓ lopinavir/ritonavir | Concomitant use of elagolix 200 mg twice daily and KALETRA for more than 1 month is not recommended due to potential risk of adverse events such as bone loss and hepatic transaminase elevations. Limit concomitant use of elagolix 150 mg once daily and KALETRA to 6 months.
Hepatitis C direct acting antiviral: elbasvir/grazoprevir | ↑ elbasvir/grazoprevir | Contraindicated due to increased risk of alanine transaminase (ALT) elevations [see Contraindications (4)] .
Hepatitis C direct acting antivirals: boceprevir* glecaprevir/pibrentasvir simeprevir sofosbuvir/velpatasvir/voxilaprevir ombitasvir/paritaprevir/ ritonavir and dasabuvir* | ↓ lopinavir ↓ boceprevir ↓ ritonavir ↑glecaprevir ↑ pibrentasvir ↑ simeprevir ↑ sofosbuvir ↑ velpatasvir ↑ voxilaprevir ↑ ombitasvir ↑ paritaprevir ↑ ritonavir ↔ dasabuvir | It is not recommended to co-administer KALETRA and boceprevir, glecaprevir/pibrentasvir, simeprevir, sofosbuvir/velpatasvir/voxilaprevir, or ombitasvir/paritaprevir/ritonavir and dasabuvir.
Herbal Products: St. John's Wort (hypericum perforatum) | ↓ lopinavir | Contraindicated due to potential for loss of virologic response and possible resistance to KALETRA or to the class of protease inhibitors [see Contraindications (4)] .
Lipid-modifying agents HMG-CoA Reductase Inhibitors: lovastatin simvastatin atorvastatin rosuvastatin Microsomal triglyceride transfer protein (MTTP) Inhibitor: lomitapide | ↑ lovastatin ↑ simvastatin ↑ atorvastatin ↑ rosuvastatin ↑ lomitapide | Contraindicated due to potential for myopathy including rhabdomyolysis [see Contraindications (4)] . Use atorvastatin with caution and at the lowest necessary dose. Titrate rosuvastatin dose carefully and use the lowest necessary dose; do not exceed rosuvastatin 10 mg/day. Lomitapide is a sensitive substrate for CYP3A4 metabolism. CYP3A4 inhibitors increase the exposure of lomitapide, with strong inhibitors increasing exposure approximately 27-fold. Concomitant use of moderate or strong CYP3A4 inhibitors with lomitapide is contraindicated due to potential for hepatotoxicity [see Contraindications (4)] .
Immunosuppressants: e.g. cyclosporine, tacrolimus, sirolimus | ↑ immunosuppressants | Therapeutic concentration monitoring is recommended for immunosuppressant agents when co-administered with KALETRA.
Kinase Inhibitors: fostamatinib (also see anticancer agents above) | ↑ fostamatinib metabolite R406 | Monitor for toxicities of R406 such as hepatotoxicity and neutropenia. Fostamatinib dose reduction may be required.
Long-acting beta-adrenoceptor Agonist: salmeterol | ↑ salmeterol | Concurrent administration of salmeterol and KALETRA is not recommended. The combination may result in increased risk of cardiovascular adverse events associated with salmeterol, including QT prolongation, palpitations and sinus tachycardia.
Narcotic Analgesics: methadone,* fentanyl | ↓ methadone ↑ fentanyl | Dosage of methadone may need to be increased when co-administered with KALETRA. Careful monitoring of therapeutic and adverse effects (including potentially fatal respiratory depression) is recommended when fentanyl is concomitantly administered with KALETRA.
PDE5 inhibitors: avanafil, sildenafil, tadalafil, vardenafil | ↑ avanafil ↑ sildenafil ↑ tadalafil ↑ vardenafil | Sildenafil when used for the treatment of pulmonary arterial hypertension (Revatio®) is contraindicated due to the potential for sildenafil-associated adverse events, including visual abnormalities, hypotension, prolonged erection, and syncope [see Contraindications (4)] . Do not use KALETRA with avanafil because a safe and effective avanafil dosage regimen has not been established. Particular caution should be used when prescribing sildenafil, tadalafil, or vardenafil in patients receiving KALETRA. Co-administration of KALETRA with these drugs may result in an increase in PDE5 inhibitor associated adverse reactions including hypotension, syncope, visual changes and prolonged erection. Use of PDE5 inhibitors for pulmonary arterial hypertension (PAH): Sildenafil (Revatio®) is contraindicated [see Contraindications (4)] . The following dose adjustments are recommended for use of tadalafil (Adcirca®) with KALETRA: Co-administration of ADCIRCA in patients on KALETRA: In patients receiving KALETRA for at least one week, start ADCIRCA at 20 mg once daily. Increase to 40 mg once daily based upon individual tolerability. Co-administration of KALETRA in patients on ADCIRCA: Avoid use of ADCIRCA during the initiation of KALETRA. Stop ADCIRCA at least 24 hours prior to starting KALETRA. After at least one week following the initiation of KALETRA, resume ADCIRCA at 20 mg once daily. Increase to 40 mg once daily based upon individual tolerability. Use of PDE5 inhibitors for erectile dysfunction: It is recommended not to exceed the following doses: • Sildenafil: 25 mg every 48 hours • Tadalafil: 10 mg every 72 hours • Vardenafil: 2.5 mg every 72 hours Use with increased monitoring for adverse events.
Sedative/Hypnotics: triazolam, orally administered midazolam | ↑ triazolam ↑ midazolam | Contraindicated due to potential for prolonged or increased sedation or respiratory depression [see Contraindications (4)] .
Sedative/Hypnotics: parenterally administered midazolam | ↑ midazolam | If KALETRA is co-administered with parenteral midazolam, close clinical monitoring for respiratory depression and/or prolonged sedation should be exercised and dosage adjustment should be considered.
Systemic/Inhaled/ Nasal/Ophthalmic Corticosteroids: e.g., betamethasone budesonide ciclesonide dexamethasone fluticasone methylprednisolone mometasone prednisone triamcinolone | ↓ lopinavir ↑ glucocorticoids | Coadministration with oral dexamethasone or other systemic corticosteroids that induce CYP3A may result in loss of therapeutic effect and development of resistance to lopinavir. Consider alternative corticosteroids. Coadministration with corticosteroids whose exposures are significantly increased by strong CYP3A inhibitors can increase the risk for Cushing’s syndrome and adrenal suppression. Alternative corticosteroids including beclomethasone and prednisolone (whose PK and/or PD are less affected by strong CYP3A inhibitors relative to other studied steroids) should be considered, particularly for long-term use.
* see Clinical Pharmacology (12.3) for magnitude of interaction.
# refers to interaction with apalutamide.

7.4 Drugs with No Observed or Predicted Interactions with KALETRA

Drug interaction or clinical studies reveal no clinically significant interaction between KALETRA and desipramine (CYP2D6 probe), etravirine, pitavastatin, pravastatin, stavudine, lamivudine, omeprazole, raltegravir, ranitidine, or rilpivirine.

Based on known metabolic profiles, clinically significant drug interactions are not expected between KALETRA and dapsone, trimethoprim/sulfamethoxazole, azithromycin, erythromycin, or fluconazole.

8 USE IN SPECIFIC POPULATIONS

8.1 Pregnancy

Pregnancy Exposure Registry

There is a pregnancy exposure registry that monitors pregnancy outcomes in women exposed to KALETRA during pregnancy. Physicians are encouraged to register patients by calling the Antiretroviral Pregnancy Registry at 1-800-258-4263.

Risk Summary

Available data from the Antiretroviral Pregnancy Registry show no difference in the risk of overall major birth defects compared to the background rate for major birth defects of 2.7% in the U.S. reference population of the Metropolitan Atlanta Congenital Defects Program (MACDP) (see Data). The estimated background rate of miscarriage in clinically recognized pregnancies in the U.S. general population is 15-20%. The background risk for major birth defects and miscarriage for the indicated population is unknown. Methodological limitations of the APR include the use of MACDP as the external comparator group. The MACDP population is not disease-specific, evaluates women and infants from a limited geographic area, and does not include outcomes for births that occurred at <20 weeks gestation (see Data). No treatment-related malformations were observed when lopinavir in combination with ritonavir was administered to pregnant rats or rabbits; however embryonic and fetal developmental toxicities occurred in rats administered maternally toxic doses.

Clinical Considerations

Dose Adjustments During Pregnancy and the Postpartum Period

Administer 400/100 mg of KALETRA twice daily in pregnant patients with no documented lopinavir-associated resistance substitutions [see Dosage and Administration (2.5) and Clinical Pharmacology (12.3)] . There are insufficient data to recommend KALETRA dosing for pregnant patients with any documented lopinavir-associated resistance substitutions. No dose adjustment of KALETRA is required for patients during the postpartum period.

Once daily KALETRA dosing is not recommended in pregnancy.

Avoid use of KALETRA oral solution during pregnancy due to the ethanol content. KALETRA oral solution contains the excipients ethanol, approximately 42% (v/v and propylene glycol, approximately 15%.

Data

Human Data

KALETRA was evaluated in 12 HIV-infected pregnant women in an open-label pharmacokinetic trial [see Clinical Pharmacology (12.3)] . No new trends in the safety profile were identified in pregnant women dosed with KALETRA compared to the safety described in non-pregnant adults, based on the review of these limited data.

Antiretroviral Pregnancy Registry Data: Based on prospective reports from the Antiretroviral Pregnancy Registry (APR) of over 3,000 exposures to lopinavir containing regimens (including over 1,000 exposed in the first trimester), there was no difference between lopinavir and overall birth defects compared with the background birth defect rate of 2.7% in the U.S. reference population of the Metropolitan Atlanta Congenital Defects Program. The prevalence of birth defects in live births was 2.1% (95% CI: 1.4%-3.0%) following first-trimester exposure to lopinavir-containing regimens and 3.0% (95% CI: 2.4%-3.8%) following second and third trimester exposure to lopinavir-containing regimens. Based on prospective reports from the APR of over 5,000 exposures to ritonavir containing regimens (including over 2,000 exposures in the first trimester) there was no difference between ritonavir and overall birth defects compared with the U.S. background rate (MACDP). The prevalence of birth defects in live births was 2.2% (95% CI: 1.7%-2.8%) following first-trimester exposure to ritonavir-containing regimens and 2.9% (95% CI: 2.4%-3.6%) following second and third trimester exposure to ritonavir-containing regimens. For both lopinavir and ritonavir, sufficient numbers of first trimester exposures have been monitored to detect at least a 1.5 fold increase in risk of overall birth defects and a 2 fold increase in risk of birth defects in the cardiovascular and genitourinary systems.

Animal Data

Embryonic and fetal developmental toxicities (early resorption, decreased fetal viability, decreased fetal body weight, increased incidence of skeletal variations and skeletal ossification delays) occurred in rats administered lopinavir in combination with ritonavir (on gestation days 6-17) at a maternally toxic dosage. Based on AUC measurements, the drug exposures in rats at the toxic doses were approximately 0.7 times (for lopinavir) and 1.8 times (for ritonavir) the exposures in humans at the recommended therapeutic dose (400/100 mg twice daily). In a pre- and post-natal study in rats, a developmental toxicity (a decrease in survival in pups between birth and postnatal Day 21) occurred.

No embryonic and fetal developmental toxicities were observed in rabbits administered lopinavir in combination with ritonavir (on gestation days 6-18) at a maternally toxic dosage. Based on AUC measurements, the drug exposures in rabbits at the toxic doses were approximately 0.6 times (for lopinavir) and similar to (for ritonavir) the exposures in humans at the recommended therapeutic dose (400/100 mg twice daily).

8.2 Lactation

Risk Summary

The Centers for Disease Control and Prevention recommend that HIV-1 infected mothers not breastfeed their infants to avoid risking postnatal transmission of HIV-1. Because of the potential for: 1) HIV transmission (in HIV-negative infants), 2) developing viral resistance (in HIV- positive infants), and 3) adverse reactions in the breastfed infant, instruct mothers not to breastfeed if they are receiving KALETRA.

8.3 Females and Males of Reproductive Potential

Contraception

Use of KALETRA may reduce the efficacy of combined hormonal contraceptives. Advise patients using combined hormonal contraceptives to use an effective alternative contraceptive method or an additional barrier method of contraception [see Drug Interactions (7.3)] .

8.4 Pediatric Use

The safety, efficacy, and pharmacokinetic profiles of KALETRA in pediatric patients below the age of 14 days have not been established. KALETRA should not be administered once daily in pediatric patients.

An open-label, multi-center, dose-finding trial was performed to evaluate the pharmacokinetic profile, tolerability, safety and efficacy of KALETRA oral solution containing lopinavir 80 mg/mL and ritonavir 20 mg/mL at a dose of 300/75 mg/m^2 twice daily plus two NRTIs in HIV-infected infants ≥14 days and < 6 months of age. Results revealed that infants younger than 6 months of age generally had lower lopinavir AUC12 than older children (6 months to 12 years of age), however, despite the lower lopinavir drug exposure observed, antiviral activity was demonstrated as reflected in the proportion of subjects who achieved HIV-1 RNA <400 copies/mL at Week 24 [see Adverse Reactions (6.2), Clinical Pharmacology (12.3), Clinical Studies (14.4)] .

Safety and efficacy in pediatric patients > 6 months of age was demonstrated in a clinical trial in 100 patients. The clinical trial was an open-label, multicenter trial evaluating the pharmacokinetic profile, tolerability, safety, and efficacy of KALETRA oral solution containing lopinavir 80 mg/mL and ritonavir 20 mg/mL in 100 antiretroviral naïve and experienced pediatric patients ages 6 months to 12 years. Dose selection for patients 6 months to 12 years of age was based on the following results. The 230/57.5 mg/m^2 oral solution twice daily regimen without nevirapine and the 300/75 mg/m^2 oral solution twice daily regimen with nevirapine provided lopinavir plasma concentrations similar to those obtained in adult patients receiving the 400/100 mg twice daily regimen (without nevirapine) [see Adverse Reactions (6.2), Clinical Pharmacology (12.3), Clinical Studies (14.4)] .

A prospective multicenter, open-label trial evaluated the pharmacokinetic profile, tolerability, safety and efficacy of high-dose KALETRA with or without concurrent NNRTI therapy (Group 1: 400/100 mg/m^2 twice daily + ≥ 2 NRTIs; Group 2: 480/120 mg/m^2 twice daily + ≥ 1 NRTI + 1 NNRTI) in 26 children and adolescents ≥ 2 years to < 18 years of age who had failed prior therapy. Patients also had saquinavir mesylate added to their regimen. This strategy was intended to assess whether higher than approved doses of KALETRA could overcome protease inhibitor cross-resistance. High doses of KALETRA exhibited a safety profile similar to those observed in previous trials; changes in HIV-1 RNA were less than anticipated; three patients had HIV-1 RNA <400 copies/mL at Week 48. CD4+ cell count increases were noted in the eight patients who remained on treatment for 48 weeks [see Adverse Reactions (6.2), Clinical Pharmacology (12.3)] .

A prospective multicenter, randomized, open-label study evaluated the efficacy and safety of twice-daily versus once-daily dosing of KALETRA tablets dosed by weight as part of combination antiretroviral therapy (cART) in virologically suppressed HIV-1 infected children (n=173). Children were eligible when they were aged < 18 years, ≥ 15 kg in weight, receiving cART that included KALETRA, HIV-1 ribonucleic acid (RNA) < 50 copies/mL for at least 24 weeks and able to swallow tablets. At week 24, efficacy (defined as the proportion of subjects with plasma HIV-1 RNA less than 50 copies per mL) was significantly higher in subjects receiving twice daily dosing compared to subjects receiving once daily dosing. The safety profile was similar between the two treatment arms although there was a greater incidence of diarrhea in the once daily treated subjects.

8.5 Geriatric Use

Clinical studies of KALETRA did not include sufficient numbers of subjects aged 65 and over to determine whether they respond differently from younger subjects. In general, appropriate caution should be exercised in the administration and monitoring of KALETRA in elderly patients reflecting the greater frequency of decreased hepatic, renal, or cardiac function, and of concomitant disease or other drug therapy.

8.6 Hepatic Impairment

KALETRA is principally metabolized by the liver; therefore, caution should be exercised when administering this drug to patients with hepatic impairment, because lopinavir concentrations may be increased [see Warnings and Precautions (5.4) and Clinical Pharmacology (12.3)] .

10 OVERDOSAGE

Overdoses with KALETRA oral solution have been reported. One of these reports described fatal cardiogenic shock in a 2.1 kg infant who received a single dose of 6.5 mL of KALETRA oral solution (520 mg lopinavir, approximately 10-fold above the recommended lopinavir dose) nine days prior. The following events have been reported in association with unintended overdoses in preterm neonates: complete AV block, cardiomyopathy, lactic acidosis, and acute renal failure [see Warnings and Precautions (5.2)] . Healthcare professionals should be aware that KALETRA oral solution is highly concentrated and therefore, should pay special attention to accurate calculation of the dose of KALETRA, transcription of the medication order, dispensing information and dosing instructions to minimize the risk for medication errors and overdose. This is especially important for infants and young children.

KALETRA oral solution contains approximately 42% (v/v) ethanol and approximately 15% (w/v) propylene glycol. Ingestion of the product over the recommended dose by an infant or a young child could result in significant toxicity and could potentially be lethal.

Human experience of acute overdosage with KALETRA is limited. Treatment of overdose with KALETRA should consist of general supportive measures including monitoring of vital signs and observation of the clinical status of the patient. There is no specific antidote for overdose with KALETRA. If indicated, elimination of unabsorbed drug should be achieved by gastric lavage. Administration of activated charcoal may also be used to aid in removal of unabsorbed drug. Since lopinavir is highly protein bound, dialysis is unlikely to be beneficial in significant removal of the drug. However, dialysis can remove both ethanol and propylene glycol in the case of overdose with KALETRA oral solution.

11 DESCRIPTION

KALETRA is a co-formulation of lopinavir and ritonavir. Lopinavir is an inhibitor of the HIV-1 protease. As co-formulated in KALETRA, ritonavir inhibits the CYP3A-mediated metabolism of lopinavir, thereby providing increased plasma levels of lopinavir.

Lopinavir is chemically designated as [1 S-[1 R*,(R*), 3 R*, 4 R*]]- N-[4-[[(2,6-dimethylphenoxy)acetyl]amino]-3-hydroxy-5-phenyl-1-(phenylmethyl)pentyl]tetrahydro-alpha-(1-methylethyl)-2-oxo-1(2 H)-pyrimidineacetamide. Its molecular formula is C37H48N4O5, and its molecular weight is 628.80. Lopinavir is a white to light tan powder. It is freely soluble in methanol and ethanol, soluble in isopropanol and practically insoluble in water. Lopinavir has the following structural formula:

Ritonavir is chemically designated as 10-hydroxy-2-methyl-5-(1-methylethyl)-1- [2-(1-methylethyl)-4-thiazolyl]-3,6-dioxo-8,11-bis(phenylmethyl)-2,4,7,12-tetraazatridecan-13-oic acid, 5-thiazolylmethyl ester, [5 S-(5 R*,8 R*,10 R*,11 R*)]. Its molecular formula is C37H48N6O5S2, and its molecular weight is 720.95. Ritonavir is a white to light tan powder. It is freely soluble in methanol and ethanol, soluble in isopropanol and practically insoluble in water. Ritonavir has the following structural formula:

KALETRA tablets are available for oral administration in two strengths:

- Yellow or red tablets containing 200 mg of lopinavir and 50 mg of ritonavir
- Pale yellow or pink tablets containing 100 mg of lopinavir and 25 mg of ritonavir.

The yellow, 200 mg lopinavir and 50 mg ritonavir, tablets contain the following inactive ingredients: colloidal silicon dioxide, copovidone, sodium stearyl fumarate and sorbitan monolaurate. The following are the ingredients in the film coating: colloidal silicon dioxide, hydroxypropyl cellulose, hypromellose, polyethylene glycol 400, polyethylene glycol 3350, polysorbate 80, talc, titanium dioxide, and yellow ferric oxide E172.

The red, 200 mg lopinavir and 50 mg ritonavir, tablets contain the following inactive ingredients: colloidal silicon dioxide, copovidone, sodium stearyl fumarate and sorbitan monolaurate. The following are the ingredients in the film coating: colloidal silicon dioxide, hydroxypropyl cellulose, hypromellose, polyethylene glycol 400, polyethylene glycol 3350, polysorbate 80, talc, titanium dioxide, and red ferric oxide E172.

The pale yellow, 100 mg lopinavir and 25 mg ritonavir, tablets contain the following inactive ingredients: colloidal silicon dioxide, copovidone, sodium stearyl fumarate, and sorbitan monolaurate. The following are the ingredients in the film coating: polyethylene glycol 3350, polyvinyl alcohol, talc, titanium dioxide, and yellow ferric oxide E172.

The pink, 100 mg lopinavir and 25 mg ritonavir, tablets contain the following inactive ingredients: colloidal silicon dioxide, copovidone, sodium stearyl fumarate, and sorbitan monolaurate. The following are the ingredients in the film coating: polyethylene glycol 3350, polyvinyl alcohol, talc, titanium dioxide, and red ferric oxide E172.

KALETRA oral solution is available for oral administration as 80 mg lopinavir and 20 mg ritonavir per milliliter with the following inactive ingredients: acesulfame potassium, artificial cotton candy flavor, citric acid, ethanol, glycerin, high fructose corn syrup, Magnasweet-110 flavor, menthol, natural & artificial vanilla flavor, peppermint oil, polyoxyl 40 hydrogenated castor oil, povidone, propylene glycol, saccharin sodium, sodium chloride, sodium citrate, and water.

KALETRA oral solution contains approximately 42% (v/v) ethanol and approximately 15% (w/v) propylene glycol.

12 CLINICAL PHARMACOLOGY

12.1 Mechanism of Action

KALETRA is a fixed-dose combination of HIV-1 antiviral drugs lopinavir [see Microbiology (12.4)] and ritonavir. As co-formulated in KALETRA, ritonavir inhibits the CYP3A-mediated metabolism of lopinavir, thereby providing increased plasma levels of lopinavir.

12.2 Pharmacodynamics

Cardiac Electrophysiology

The effect of KALETRA on QTcF interval was evaluated in a placebo and active (moxifloxacin 400 mg once daily) controlled crossover study in 39 healthy adults. The maximum mean time-matched (95% upper confidence bound) differences in QTcF interval from placebo after baseline-correction were 5.3 (8.1) and 15.2 (18.0) mseconds (msec) for 400/100 mg twice daily and supratherapeutic 800/200 mg twice daily KALETRA, respectively. KALETRA 800/200 mg twice daily resulted in a Day 3 mean Cmax approximately 2-fold higher than the mean Cmax observed with the approved once daily and twice daily KALETRA doses at steady state. The maximum mean (95% upper confidence bound) difference from placebo in the PR interval after baseline-correction were 24.9 (21.5, 28.3) and 31.9 (28.5, 35.3) msec for 400/100 mg twice daily and supratherapeutic 800/200 mg twice daily KALETRA, respectively [see Warnings and Precautions (5.5, 5.6)] .

12.3 Pharmacokinetics

The pharmacokinetic properties of lopinavir are summarized in Table 13. The steady-state pharmacokinetic parameters of lopinavir are summarized in Table 14. Under fed conditions, lopinavir concentrations were similar following administration of KALETRA tablets to capsules with less pharmacokinetic variability. Under fed conditions (500 kcal, 25% from fat), lopinavir concentrations were similar following administration of KALETRA capsules and oral solution.

Table 13. Pharmacokinetic Properties of Lopinavir
Absorption
Tmax (hr)a | 4.4 ± 0.8
Effect of meal (relative to fasting) Tablet Oral solution | ↑ 19%b ↑ 130%b
Distribution
% Bound to human plasma proteins | > 98
Vd/Fa (L) | 16.9
Metabolism
Metabolism | CYP3A
Elimination
Major route of elimination | hepatic
t1/2 (h)a | 6.9 ± 2.2
% of dose excreted in urine | 10.4 ± 2.3
% of dose excreted in feces | 82.6 ± 2.5
a. Kaletra tablet
b. Changes in AUC values

Table 14. Steady-State Pharmacokinetic Parameters of Lopinavir, Mean ± SD
Pharmacokinetic Parameter | Twice Dailya | Once Dailyb
Cmax (µg/mL) | 9.8 ± 3.7 | 11.8 ± 3.7
Cmin (µg/mL) | 5.5 ± 2.7 | 1.7 ± 1.6
AUCtau (µg•h/mL) | 92.6 ± 36.7 | 154.1 ± 61.4
1. 19 HIV-1 subjects, Kaletra 400/100 mg twice daily
2. 24 HIV-1 subjects, Kaletra 800/200 mg + emtricitabine 200 mg + tenofovir DF 300 mg

Specific Populations

Gender, Race and Age

No gender or race related pharmacokinetic differences have been observed in adult patients. Lopinavir pharmacokinetics have not been studied in elderly patients.

Pediatric Patients

The 230/57.5 mg/m^2 twice daily regimen without nevirapine and the 300/75 mg/m^2 twice daily regimen with nevirapine provided lopinavir plasma concentrations similar to those obtained in adult patients receiving the 400/100 mg twice daily regimen without nevirapine.

Table 15. Lopinavir Pharmacokinetic Data from Pediatric Clinical Trials, Mean ± SD
Cmax (μg/mL) | Cmin (μg/mL) | AUC12 (μg•hr/m)
Age ≥ 14 Days to < 6 Weeks Cohort (N = 9):
5.17 ± 1.84a | 1.40 ± 0.48a | 43.39 ± 14.80a
Age ≥ 6 Weeks to < 6 Months Cohort (N = 18):
9.39 ± 4.91a | 1.95 ± 1.80a | 74.50 ± 37.87a
Age ≥ 6 Months to ≤ 12 years Cohort (N = 24):
8.2 ± 2.9b | 3.4 ± 2.1b | 72.6 ± 31.1b
10.0 ± 3.3c | 3.6 ± 3.5c | 85.8 ± 36.9c
1. KALETRA oral solution300/75 mg/m^2 twice daily without concomitant NNRTI therapy
2. KALETRA oral solution 230/57.5 mg/m^2 twice daily without nevirapine (n=12)
3. KALETRA oral solution 300/75 mg/m^2 twice daily with nevirapine (n=12)

Pregnancy

The C12h values of lopinavir were lower during the second and third trimester by approximately 40% as compared to post-partum in 12 HIV-infected pregnant women received KALETRA 400 mg/100 mg twice daily. Yet this decrease is not considered clinically relevant in patients with no documented KALETRA-associated resistance substitutions receiving 400 mg/100 mg twice daily [see Use in Specific Populations (8.1)] .

Renal Impairment

Lopinavir pharmacokinetics have not been studied in patients with renal impairment; however, since the renal clearance of lopinavir is negligible, a decrease in total body clearance is not expected in patients with renal impairment.

Hepatic Impairment

Multiple dosing of KALETRA 400/100 mg twice daily to HIV-1 and HCV co-infected patients with mild to moderate hepatic impairment (n = 12) resulted in a 30% increase in lopinavir AUC and 20% increase in Cmax compared to HIV-1 infected subjects with normal hepatic function (n = 12). Additionally, the plasma protein binding of lopinavir was statistically significantly lower in both mild and moderate hepatic impairment compared to controls (99.09 vs. 99.31%, respectively). KALETRA has not been studied in patients with severe hepatic impairment [see Warnings and Precautions (5.4) and Use in Specific Populations (8.6)] .

Drug Interactions

KALETRA is an inhibitor of the P450 isoform CYP3A in vitro. KALETRA does not inhibit CYP2D6, CYP2C9, CYP2C19, CYP2E1, CYP2B6 or CYP1A2 at clinically relevant concentrations.

KALETRA has been shown in vivo to induce its own metabolism and to increase the biotransformation of some drugs metabolized by cytochrome P450 enzymes and by glucuronidation.

The effects of co-administration of KALETRA on the AUC, Cmax and Cmin are summarized in Table 16 (effect of other drugs on lopinavir) and Table 17 (effect of KALETRA on other drugs). For information regarding clinical recommendations, see Table 12 in Drug Interactions (7) .

Table 16. Drug Interactions: Pharmacokinetic Parameters for Lopinavir in the Presence of the Co-administered Drug for Recommended Alterations in Dose or Regimen
Co- administered Drug | Dose of Co- administered Drug (mg) | Dose of KALETRA (mg) | n | Ratio (in combination with Co-administered drug/alone) of Lopinavir Pharmacokinetic Parameters (90% CI); No Effect = 1.00
 |  |  |  | Cmax | AUC | Cmin
Efavirenz^1 | 600 at bedtime | 400/100 capsule twice daily | 11, 7^3 | 0.97 (0.78, 1.22) | 0.81 (0.64, 1.03) | 0.61 (0.38, 0.97)
 | 600 at bedtime | 500/125 tablet twice daily | 19 | 1.12 (1.02, 1.23) | 1.06 (0.96, 1.17) | 0.90 (0.78, 1.04)
 | 600 at bedtime | 600/150 tablet twice daily | 23 | 1.36 (1.28, 1.44) | 1.36 (1.28, 1.44) | 1.32 (1.21, 1.44)
Etravirine | 200 twice daily | 400/100 mg twice day (tablets) | 16 | 0.89 (0.82-0.96) | 0.87 (0.83-0.92) | 0.80 (0.73-0.88)
Fosamprenavir^2 | 700 twice daily plus ritonavir 100 twice daily | 400/100 capsule twice daily | 18 | 1.30 (0.85, 1.47) | 1.37 (0.80, 1.55) | 1.52 (0.72, 1.82)
Ketoconazole | 200 single dose | 400/100 capsule twice daily | 12 | 0.89 (0.80, 0.99) | 0.87 (0.75, 1.00) | 0.75 (0.55, 1.00)
Nelfinavir | 1000 twice daily | 400/100 capsule twice daily | 13 | 0.79 (0.70, 0.89) | 0.73 (0.63, 0.85) | 0.62 (0.49, 0.78)
Nevirapine | 200 twice daily steady-state | 400/100 capsule twice daily | 22, 19^3 | 0.81 (0.62, 1.05) | 0.73 (0.53, 0.98) | 0.49 (0.28, 0.74)
Nevirapine | 7 mg/kg or 4 mg/kg once daily; twice daily 1 wk^5 | (> 1 yr) 300/ 75 mg/m^2 oral solution twice daily | 12, 15^3 | 0.86 (0.64, 1.16) | 0.78 (0.56, 1.09) | 0.45 (0.25, 0.81)
Ombitasvir/ paritaprevir/ ritonavir+ dasabuvir^2 | 25/150/100 + dasabuvir 400 | 400/100 tablet twice daily | 6 | 0.87 (0.76, 0.99) | 0.94 (0.81, 1.10) | 1.15 (0.93, 1.42)
Omeprazole | 40 once daily, 5 d | 400/100 tablet twice daily, 10 d | 12 | 1.08 (0.99, 1.17) | 1.07 (0.99, 1.15) | 1.03 (0.90, 1.18)
Omeprazole | 40 once daily, 5 d | 800/200 tablet once daily, 10 d | 12 | 0.94 (0.88, 1.00) | 0.92 (0.86, 0.99) | 0.71 (0.57, 0.89)
Pravastatin | 20 once daily, 4 d | 400/100 capsule twice daily, 14 d | 12 | 0.98 (0.89, 1.08) | 0.95 (0.85, 1.05) | 0.88 (0.77, 1.02)
Ranitidine | 150 single dose | 400/100 tablet twice daily, 10 d | 12 | 0.99 (0.95, 1.03) | 0.97 (0.93, 1.01) | 0.90 (0.85, 0.95)
Ranitidine | 150 single dose | 800/200 tablet once daily, 10 d | 10 | 0.97 (0.95, 1.00) | 0.95 (0.91, 0.99) | 0.82 (0.74, 0.91)
Rifabutin | 150 once daily | 400/100 capsule twice daily | 14 | 1.08 (0.97, 1.19) | 1.17 (1.04, 1.31) | 1.20 (0.96, 1.65)
Rifampin | 600 once daily | 400/100 capsule twice daily | 22 | 0.45 (0.40, 0.51) | 0.25 (0.21, 0.29) | 0.01 (0.01, 0.02)
 | 600 once daily | 800/200 capsule twice daily | 10 | 1.02 (0.85, 1.23) | 0.84 (0.64, 1.10) | 0.43 (0.19, 0.96)
 | 600 once daily | 400/400 capsule twice daily | 9 | 0.93 (0.81, 1.07) | 0.98 (0.81, 1.17) | 1.03 (0.68, 1.56)
Rilpivirine | 150 once daily | 400/100 twice daily (capsules) | 15 | 0.96 (0.88-1.05) | 0.99 (0.89-1.10) | 0.89 (0.73-1.08)
Ritonavir | 100 twice daily | 400/100 capsule twice daily | 8, 21^3 | 1.28 (0.94, 1.76) | 1.46 (1.04, 2.06) | 2.16 (1.29, 3.62)
Tipranavir/ ritonavir | 500/200 twice daily | 400/100 capsule twice daily | 21 69^3 | 0.53 (0.40, 0.69) | 0.45 (0.32, 0.63) | 0.30 (0.17, 0.51) 0.48^4 (0.40, 0.58)
1 Reference for comparison is lopinavir/ritonavir 400/100 mg twice daily without efavirenz.
2 Data extracted from the U.S. prescribing information of co-administered drugs.
3 Parallel group design
4 Drug levels obtained at 8-16 hours post dose
N/A = Not available.

Table 17. Drug Interactions: Pharmacokinetic Parameters for Co-administered Drug in the Presence of KALETRA for Recommended Alterations in Dose or Regimen
Co- administered Drug | Dose of Co- administered Drug (mg) | Dose of KALETRA (mg) | n | Ratio (in combination with KALETRA/alone) of Co- administered Drug Pharmacokinetic Parameters (90% CI); No Effect = 1.00
 |  |  |  | Cmax | AUC | Cmin
Bedaquiline^1 | 400 single dose | 400/100 twice daily | N/A | N/A | 1.22 (1.11, 1.34) | N/A
Efavirenz | 600 at bedtime | 400/100 capsule twice daily | 11, 12^3 | 0.91 (0.72, 1.15) | 0.84 (0.62, 1.15) | 0.84 (0.58, 1.20)
Elbasvir/ grazoprevir^1 | 50 once daily | 400/100 twice daily | 10 | 2.87 (2.29, 3.58) | 3.71 (3.05, 4.53) | 4.58 (3.72, 5.64)
 | 200 once daily | 400/100 twice daily | 13 | 7.31 (5.65, 9.45) | 12.86 (10.25, 16.13) | 21.70 (12.99, 36.25)
Ethinyl Estradiol | 35 µg once daily (Ortho Novum®) | 400/100 capsule twice daily | 12 | 0.59 (0.52, 0.66) | 0.58 (0.54, 0.62) | 0.42 (0.36, 0.49)
Etravirine | 200 twice daily | 400/100 tablet twice day | 16 | 0.70 (0.64-0.78) | 0.65 (0.59-0.71) | 0.55 (0.49-0.62)
Fosamprenavir^1 | 700 twice daily plus ritonavir 100 twice daily | 400/100 capsule twice daily | 18 | 0.42 (0.30, 0.58) | 0.37 (0.28, 0.49) | 0.35 (0.27, 0.46)
Indinavir | 600 twice daily combo nonfasting vs. 800 three times daily alone fasting | 400/100 capsule twice daily | 13 | 0.71 (0.63, 0.81) | 0.91 (0.75, 1.10) | 3.47 (2.60, 4.64)
Ketoconazole | 200 single dose | 400/100 capsule twice daily | 12 | 1.13 (0.91, 1.40) | 3.04 (2.44, 3.79) | N/A
Maraviroc^1 | 300 twice daily | 400/100 twice daily | 11 | 1.97 (1.66, 2.34) | 3.95 (3.43, 4.56) | 9.24 (7.98, 10.7)
Methadone | 5 single dose | 400/100 capsule twice daily | 11 | 0.55 (0.48, 0.64) | 0.47 (0.42, 0.53) | N/A
Nelfinavir | 1000 twice daily combo vs. 1250 twice daily alone | 400/100 capsule twice daily | 13 | 0.93 (0.82, 1.05) | 1.07 (0.95, 1.19) | 1.86 (1.57, 2.22)
M8 metabolite |  |  |  | 2.36 (1.91, 2.91) | 3.46 (2.78, 4.31) | 7.49 (5.85, 9.58)
Nevirapine | 200 once daily twice daily | 400/100 capsule twice daily | 5, 6^3 | 1.05 (0.72, 1.52) | 1.08 (0.72, 1.64) | 1.15 (0.71, 1.86)
Norethindrone | 1 once daily (Ortho Novum®) | 400/100 capsule twice daily | 12 | 0.84 (0.75, 0.94) | 0.83 (0.73, 0.94) | 0.68 (0.54, 0.85)
Ombitasvir/ paritaprevir/ ritonavir+ dasabuvir^1 | 25/150/100 + dasabuvir 400 | 400/100 tablet twice daily | 6 | 1.14 (1.01, 1.28) | 1.17 (1.07, 1.28) | 1.24 (1.14, 1.34)
Ombitasvir/ paritaprevir/ ritonavir+ dasabuvir^1 | 25/150/100 + dasabuvir 400 | 400/100 tablet twice daily | 6 | 2.04 (1.30, 3.20) | 2.17 (1.63, 2.89) | 2.36 (1.00, 5.55)
Ombitasvir/ paritaprevir/ ritonavir+ dasabuvir^1 | 25/150/100 + dasabuvir 400 | 400/100 tablet twice daily | 6 | 1.55 (1.16, 2.09) | 2.05 (1.49, 2.81) | 5.25 (3.33, 8.28)
Ombitasvir/ paritaprevir/ ritonavir+ dasabuvir^1 | 25/150/100 + dasabuvir 400 | 400/100 tablet twice daily | 6 | 0.99 (0.75, 1.31) | 0.93 (0.75, 1.15) | 0.68 (0.57, 0.80)
Pitavastatin^1 | 4 once daily | 400/100 tablet twice daily | 23 | 0.96 (0.84-1.10) | 0.80 (0.73-0.87) | N/A
Pravastatin | 20 once daily | 400/100 capsule twice daily | 12 | 1.26 (0.87, 1.83) | 1.33 (0.91, 1.94) | N/A
Rifabutin | 150 once daily combo vs. 300 once daily alone | 400/100 capsule twice daily | 12 | 2.12 (1.89, 2.38) | 3.03 (2.79, 3.30) | 4.90 (3.18, 5.76)
25- O-desacetyl rifabutin |  |  |  | 23.6 (13.7, 25.3) | 47.5 (29.3, 51.8) | 94.9 (74.0, 122)
Rifabutin + 25- O-desacetyl rifabutin |  |  |  | 3.46 (3.07, 3.91) | 5.73 (5.08, 6.46) | 9.53 (7.56, 12.01)
Rilpivirine | 150 once daily | 400/100 capsules twice daily | 15 | 1.29 (1.18-1.40) | 1.52 (1.36-1.70) | 1.74 (1.46-2.08)
Rosuvastatin^2 | 20 once daily | 400/100 tablet twice daily | 15 | 4.66 (3.4, 6.4) | 2.08 (1.66, 2.6) | 1.04 (0.9, 1.2)
Tenofovir alafenamide^1 | 10 once daily | 800/200 tablet once daily | 10 | 2.19 (1.72, 2.79) | 1.47 (1.17, 1.85) | N/A
Tenofovir disoproxil fumarate^1 | 300 once daily | 400/100 capsule twice daily | 24 | No Change | 1.32 (1.26, 1.38) | 1.51 (1.32, 1.66)
1 Data extracted from the U.S. prescribing information of co-administered drugs.
2 Kiser, et al. J Acquir Immune Defic Syndr. 2008 Apr 15; 47(5):570-8.
3 Parallel group design
N/A = Not available.

12.4 Microbiology

Mechanism of Action

Lopinavir, an inhibitor of the HIV-1 protease, prevents cleavage of the viral Gag-Pol polyprotein, resulting in the production of immature, non-infectious viral particles.

Antiviral Activity

In the absence of human serum, the mean 50% effective concentration (EC50) values of lopinavir against five different HIV-1 subtype B laboratory strains in lymphoblastic cell lines ranged from 10-27 nM (0.006-0.017 µg/mL, 1 µg/mL = 1.6 µM), and ranged from 4-11 nM (0.003-0.007 µg/mL) against several HIV-1 subtype B clinical isolates in peripheral blood lymphocytes (n = 6). In the presence of 50% human serum, the mean EC50 values of lopinavir against these five HIV-1 laboratory strains ranged from 65-289 nM (0.04-0.18 µg/mL), representing a 7 to 11-fold attenuation. The EC50 values of lopinavir against three different HIV-2 strains ranged from 12-180 nM (0.008-113 μg/mL).

Resistance

HIV-1 isolates with reduced susceptibility to lopinavir have been selected in cell culture. The presence of ritonavir does not appear to influence the selection of lopinavir-resistant viruses in cell culture.

In a study of 653 antiretroviral treatment-naïve patients (Study 863), plasma viral isolates from each patient on treatment with plasma HIV-1 RNA >400 copies/mL at Week 24, 32, 40 and/or 48 were analyzed. No specific amino acid substitutions could be associated with resistance to KALETRA in the virus from 37 evaluable KALETRA-treated patients. The selection of resistance to KALETRA in antiretroviral treatment-naïve pediatric patients (Study 940) appears to be consistent with that seen in adult patients (Study 863).

Resistance to KALETRA has been noted to emerge in patients treated with other protease inhibitors prior to KALETRA therapy. In studies of 227 antiretroviral treatment-naïve and protease inhibitor experienced patients, isolates from 4 of 23 patients with quantifiable (>400 copies/mL) viral RNA following treatment with KALETRA for 12 to 100 weeks displayed significantly reduced susceptibility to lopinavir compared to the corresponding baseline viral isolates. All four of these patients had previously received treatment with at least one protease inhibitor and had at least 4 substitutions associated with protease inhibitor resistance immediately prior to KALETRA therapy. Following viral rebound, isolates from these patients all contained additional substitutions, some of which are recognized to be associated with protease inhibitor resistance.

Cross-resistance - Nonclinical Studies

Varying degrees of cross-resistance have been observed among HIV-1 protease inhibitors. The antiviral activity in cell culture of lopinavir against clinical isolates from patients previously treated with a single protease inhibitor was determined (Table 18).

Table 18. Susceptibility Reduction to Lopinavir Against Isolates from Patients Previously Treated With a Single Protease Inhibitor
Susceptibility reduced by >4 fold | Susceptibility reduced to LPV
Indinavir (n=16) | 5.7 fold
Nelfinavir (n=13) | <4 fold
Ritonavir (n=3) | 8.32 fold
Saquinavir (n=4) | <4 fold

Isolates from patients previously treated with two or more protease inhibitors showed greater reductions in susceptibility to lopinavir, as described in the following section.

Clinical Studies - Antiviral Activity of KALETRA in Patients with Previous Protease Inhibitor Therapies

The clinical relevance of reduced susceptibility in cell culture to lopinavir has been examined by assessing the virologic response to KALETRA therapy in treatment-experienced patients, with respect to baseline viral genotype in three studies and baseline viral phenotype in one study.

Virologic response to KALETRA has been shown to be affected by the presence of three or more of the following amino acid substitutions in protease at baseline: L10F/I/R/V, K20M/N/R, L24I, L33F, M36I, I47V, G48V, I54L/T/V, V82A/C/F/S/T, and I84V. Table 19 shows the 48-week virologic response (HIV-1 RNA <400 copies/mL) according to the number of the above protease inhibitor resistance-associated substitutions at baseline in studies 888 and 765 [see Clinical Studies (14.2) and (14.3)] and study 957 (see below). Once daily administration of KALETRA for adult patients with three or more of the above substitutions is not recommended.

Table 19. Virologic Response (HIV-1 RNA <400 copies/mL) at Week 48 by Baseline KALETRA Susceptibility and by Number of Protease Substitutions Associated with Reduced Response to KALETRA^1
Number of protease inhibitor substitutions at baseline^1 | Study 888 (Single protease inhibitor-experienced^2, NNRTI-naïve) n=130 | Study 765 (Single protease inhibitor-experienced^3, NNRTI-naïve) n=56 | Study 957 (Multiple protease inhibitor-experienced^4, NNRTI-naïve) n=50
0-2 | 76/103 (74%) | 34/45 (76%) | 19/20 (95%)
3-5 | 13/26 (50%) | 8/11 (73%) | 18/26 (69%)
6 or more | 0/1 (0%) | N/A | 1/4 (25%)
1 Substitutions considered in the analysis included L10F/I/R/V, K20M/N/R, L24I, L33F, M36I, I47V, G48V, I54L/T/V, V82A/C/F/S/T, and I84V.
2 43% indinavir, 42% nelfinavir, 10% ritonavir, 15% saquinavir.
3 41% indinavir, 38% nelfinavir, 4% ritonavir, 16% saquinavir.
4 86% indinavir, 54% nelfinavir, 80% ritonavir, 70% saquinavir.

Virologic response to KALETRA therapy with respect to phenotypic susceptibility to lopinavir at baseline was examined in Study 957. In this study 56 NNRTI-naïve patients with HIV-1 RNA >1,000 copies/mL despite previous therapy with at least two protease inhibitors selected from indinavir, nelfinavir, ritonavir, and saquinavir were randomized to receive one of two doses of KALETRA in combination with efavirenz and nucleoside reverse transcriptase inhibitors (NRTIs). The EC50 values of lopinavir against the 56 baseline viral isolates ranged from 0.5- to 96-fold the wild-type EC50 value. Fifty-five percent (31/56) of these baseline isolates displayed >4-fold reduced susceptibility to lopinavir. These 31 isolates had a median reduction in lopinavir susceptibility of 18-fold. Response to therapy by baseline lopinavir susceptibility is shown in Table 20.

Table 20. HIV-1 RNA Response at Week 48 by Baseline Lopinavir Susceptibility^1
Lopinavir susceptibility^2 at baseline | HIV-1 RNA <400 copies/mL (%) | HIV-1 RNA <50 copies/mL (%)
< 10 fold | 25/27 (93%) | 22/27 (81%)
> 10 and < 40 fold | 11/15 (73%) | 9/15 (60%)
≥ 40 fold | 2/8 (25%) | 2/8 (25%)
1 Lopinavir susceptibility was determined by recombinant phenotypic technology performed by Virologic.
2 Fold change in susceptibility from wild type.

13 NONCLINICAL TOXICOLOGY

13.1 Carcinogenesis, Mutagenesis, Impairment of Fertility

Carcinogenesis

Lopinavir/ritonavir combination was evaluated for carcinogenic potential by oral gavage administration to mice and rats for up to 104 weeks. Results showed an increase in the incidence of benign hepatocellular adenomas and an increase in the combined incidence of hepatocellular adenomas plus carcinoma in both males and females in mice and males in rats at doses that produced approximately 1.6-2.2 times (mice) and 0.5 times (rats) the human exposure (based on AUC0-24hr measurement) at the recommended dose of 400/100 mg KALETRA twice daily. Administration of lopinavir/ritonavir did not cause a statistically significant increase in the incidence of any other benign or malignant neoplasm in mice or rats.

Carcinogenicity studies in mice and rats have been carried out on ritonavir. In male mice, there was a dose dependent increase in the incidence of both adenomas and combined adenomas and carcinomas in the liver. Based on AUC measurements, the exposure at the high dose was approximately 4-fold for males that of the exposure in humans with the recommended therapeutic dose (400/100 mg KALETRA twice daily). There were no carcinogenic effects seen in females at the dosages tested. The exposure at the high dose was approximately 9-fold for the females that of the exposure in humans. There were no carcinogenic effects in rats. In this study, the exposure at the high dose was approximately 0.7-fold that of the exposure in humans with the 400/100 mg KALETRA twice daily regimen. Based on the exposures achieved in the animal studies, the significance of the observed effects is not known.

Mutagenesis

Neither lopinavir nor ritonavir was found to be mutagenic or clastogenic in a battery of in vitro and in vivo assays including the Ames bacterial reverse mutation assay using S. typhimurium and E. coli, the mouse lymphoma assay, the mouse micronucleus test and chromosomal aberration assays in human lymphocytes.

Impairment of Fertility

Lopinavir in combination with ritonavir at a 2:1 ratio produced no effects on fertility in male and female rats at levels of 10/5, 30/15 or 100/50 mg/kg/day. Based on AUC measurements, the exposures in rats at the high doses were approximately 0.7-fold for lopinavir and 1.8-fold for ritonavir of the exposures in humans at the recommended therapeutic dose (400/100 mg twice daily).

14 CLINICAL STUDIES

14.1 Adult Patients without Prior Antiretroviral Therapy

Study 863: KALETRA Capsules twice daily + stavudine + lamivudine compared to nelfinavir three times daily + stavudine + lamivudine

Study 863 was a randomized, double-blind, multicenter trial comparing treatment with KALETRA capsules (400/100 mg twice daily) plus stavudine and lamivudine versus nelfinavir (750 mg three times daily) plus stavudine and lamivudine in 653 antiretroviral treatment naïve patients. Patients had a mean age of 38 years (range: 19 to 84), 57% were Caucasian, and 80% were male. Mean baseline CD4+ cell count was 259 cells/mm^3 (range: 2 to 949 cells/mm^3) and mean baseline plasma HIV-1 RNA was 4.9 log10 copies/mL (range: 2.6 to 6.8 log10 copies/mL).

Treatment response and outcomes of randomized treatment are presented in Table 21.

Table 21. Outcomes of Randomized Treatment Through Week 48 (Study 863)
Outcome | KALETRA+d4T+3TC (N = 326) | Nelfinavir+d4T+3TC (N = 327)
Responder^1 | 75% | 62%
Virologic failure^2 Rebound Never suppressed through Week 48 | 9% 7% 2% | 25% 15% 9%
Death | 2% | 1%
Discontinued due to adverse events | 4% | 4%
Discontinued for other reasons^3 | 10% | 8%
1 Patients achieved and maintained confirmed HIV-1 RNA < 400 copies/mL through Week 48.
2 Includes confirmed viral rebound and failure to achieve confirmed < 400 copies/mL through Week 48.
3 Includes lost to follow-up, patient's withdrawal, non-compliance, protocol violation and other reasons. Overall discontinuation through Week 48, including patients who discontinued subsequent to virologic failure, was 17% in the KALETRA arm and 24% in the nelfinavir arm.

Through 48 weeks of therapy, there was a statistically significantly higher proportion of patients in the KALETRA arm compared to the nelfinavir arm with HIV-1 RNA < 400 copies/mL (75% vs. 62%, respectively) and HIV-1 RNA < 50 copies/mL (67% vs. 52%, respectively). Treatment response by baseline HIV-1 RNA level subgroups is presented in Table 22.

Table 22. Proportion of Responders Through Week 48 by Baseline Viral Load (Study 863)
Baseline Viral Load (HIV-1 RNA copies/mL) | KALETRA +d4T+3TC |  |  | Nelfinavir +d4T+3TC
 | <400 copies/mL^1 | <50 copies/mL^2 | n | <400 copies/mL^1 | <50 copies/mL^2 | n
< 30,000 | 74% | 71% | 82 | 79% | 72% | 87
≥ 30,000 to < 100,000 | 81% | 73% | 79 | 67% | 54% | 79
≥ 100,000 to < 250,000 | 75% | 64% | 83 | 60% | 47% | 72
≥ 250,000 | 72% | 60% | 82 | 44% | 33% | 89
1 Patients achieved and maintained confirmed HIV-1 RNA < 400 copies/mL through Week 48.
2 Patients achieved HIV-1 RNA < 50 copies/mL at Week 48.

Through 48 weeks of therapy, the mean increase from baseline in CD4+ cell count was 207 cells/mm^3 for the KALETRA arm and 195 cells/mm^3 for the nelfinavir arm.

Study 730: KALETRA Tablets once daily + tenofovir DF + emtricitabine compared to KALETRA Tablets twice daily + tenofovir DF + emtricitabine

Study 730 was a randomized, open-label, multicenter trial comparing treatment with KALETRA 800/200 mg once daily plus tenofovir DF and emtricitabine versus KALETRA 400/100 mg twice daily plus tenofovir DF and emtricitabine in 664 antiretroviral treatment-naïve patients. Patients were randomized in a 1:1 ratio to receive either KALETRA 800/200 mg once daily (n = 333) or KALETRA 400/100 mg twice daily (n = 331). Further stratification within each group was 1:1 (tablet vs. capsule). Patients administered the capsule were switched to the tablet formulation at Week 8 and maintained on their randomized dosing schedule. Patients were administered emtricitabine 200 mg once daily and tenofovir DF 300 mg once daily. Mean age of patients enrolled was 39 years (range: 19 to 71); 75% were Caucasian, and 78% were male. Mean baseline CD4+ cell count was 216 cells/mm^3 (range: 20 to 775 cells/mm^3) and mean baseline plasma HIV-1 RNA was 5.0 log10 copies/mL (range: 1.7 to 7.0 log10 copies/mL).

Treatment response and outcomes of randomized treatment through Week 48 are presented in Table 23.

Table 23. Outcomes of Randomized Treatment Through Week 48 (Study 730)
Outcome | KALETRA Once Daily + TDF + FTC (n = 333) | KALETRA Twice Daily + TDF + FTC (n = 331)
Responder^1 | 78% | 77%
Virologic failure^2 Rebound Never suppressed through Week 48 | 10% 5% 5% | 8% 5% 3%
Death | 1% | <1%
Discontinued due to adverse events | 4% | 3%
Discontinued for other reasons^3 | 8% | 11%
1 Patients achieved and maintained confirmed HIV-1 RNA < 50 copies/mL through Week 48.
2 Includes confirmed viral rebound and failure to achieve confirmed < 50 copies/mL through Week 48.
3 Includes lost to follow-up, patient's withdrawal, non-compliance, protocol violation and other reasons.

Through 48 weeks of therapy, 78% in the KALETRA once daily arm and 77% in the KALETRA twice daily arm achieved and maintained HIV-1 RNA < 50 copies/mL (95% confidence interval for the difference, -5.9% to 6.8%). Mean CD4+ cell count increases at Week 48 were 186 cells/mm^3 for the KALETRA once daily arm and 198 cells/mm^3 for the KALETRA twice daily arm.

14.2 Adult Patients with Prior Antiretroviral Therapy

Study 888: KALETRA Capsules twice daily + nevirapine + NRTIs compared to investigator-selected protease inhibitor(s) + nevirapine + NRTIs

Study 888 was a randomized, open-label, multicenter trial comparing treatment with KALETRA capsules (400/100 mg twice daily) plus nevirapine and nucleoside reverse transcriptase inhibitors versus investigator-selected protease inhibitor(s) plus nevirapine and nucleoside reverse transcriptase inhibitors in 288 single protease inhibitor-experienced, non-nucleoside reverse transcriptase inhibitor (NNRTI)-naïve patients. Patients had a mean age of 40 years (range: 18 to 74), 68% were Caucasian, and 86% were male. Mean baseline CD4+ cell count was 322 cells/mm^3 (range: 10 to 1059 cells/mm^3) and mean baseline plasma HIV-1 RNA was 4.1 log10 copies/mL (range: 2.6 to 6.0 log10 copies/mL).

Treatment response and outcomes of randomized treatment through Week 48 are presented in Table 24.

Table 24. Outcomes of Randomized Treatment Through Week 48 (Study 888)
Outcome | KALETRA + nevirapine + NRTIs (n = 148) | Investigator-Selected Protease Inhibitor(s) + nevirapine + NRTIs (n = 140)
Responder^1 | 57% | 33%
Virologic failure^2 Rebound Never suppressed through Week 48 | 24% 11% 13% | 41% 19% 23%
Death | 1% | 2%
Discontinued due to adverse events | 5% | 11%
Discontinued for other reasons^3 | 14% | 13%
1 Patients achieved and maintained confirmed HIV-1 RNA < 400 copies/mL through Week 48.
2 Includes confirmed viral rebound and failure to achieve confirmed < 400 copies/mL through Week 48.
3 Includes lost to follow-up, patient's withdrawal, non-compliance, protocol violation and other reasons.

Through 48 weeks of therapy, there was a statistically significantly higher proportion of patients in the KALETRA arm compared to the investigator-selected protease inhibitor(s) arm with HIV-1 RNA < 400 copies/mL (57% vs. 33%, respectively).

Through 48 weeks of therapy, the mean increase from baseline in CD4+ cell count was 111 cells/mm^3 for the KALETRA arm and 112 cells/mm^3 for the investigator-selected protease inhibitor(s) arm.

Study 802: KALETRA Tablets 800/200 mg Once Daily Versus 400/100 mg Twice Daily when Co-administered with Nucleoside/Nucleotide Reverse Transcriptase Inhibitors in Antiretroviral-Experienced, HIV-1 Infected Subjects

M06-802 was a randomized open-label study comparing the safety, tolerability, and antiviral activity of once daily and twice daily dosing of KALETRA tablets in 599 subjects with detectable viral loads while receiving their current antiviral therapy. Of the enrolled subjects, 55% on both treatment arms had not been previously treated with a protease inhibitor and 81 – 88% had received prior NNRTIs as part of their anti-HIV treatment regimen. Patients were randomized in a 1:1 ratio to receive either KALETRA 800/200 mg once daily (n = 300) or KALETRA 400/100 mg twice daily (n = 299). Patients were administered at least two nucleoside/nucleotide reverse transcriptase inhibitors selected by the investigator. Mean age of patients enrolled was 41 years (range: 21 to 73); 51% were Caucasian, and 66% were male. Mean baseline CD4+ cell count was 254 cells/mm^3 (range: 4 to 952 cells/mm^3) and mean baseline plasma HIV-1 RNA was 4.3 log10 copies/mL (range: 1.7 to 6.6 log10 copies/mL).

Treatment response and outcomes of randomized treatment through Week 48 are presented in Table 25.

Table 25. Outcomes of Randomized Treatment Through Week 48 (Study 802)
Outcome | KALETRA Once Daily + NRTIs (n = 300) | KALETRA Twice Daily + NRTIs (n = 299)
Virologic Success (HIV-1 RNA <50 copies/mL) | 57% | 54%
Virologic failure^1 | 22% | 24%
No virologic data in Week 48 window
Discontinued study due to adverse event or death^2 | 5% | 7%
Discontinued study for other reasons^3 | 13% | 12%
Missing data during window but on study | 3% | 3%
1 Includes patients who discontinued prior to Week 48 for lack or loss of efficacy and patients with HIV-1 RNA ≥ 50 copies/mL at Week 48.
2 Includes patients who discontinued due to adverse events or death at any time from Day 1 through Week 48 if this resulted in no virologic data on treatment at Week 48.
3 Includes withdrawal of consent, loss to follow-up, non-compliance, protocol violation and other reasons.

Through 48 weeks of treatment, the mean change from baseline for CD4 + cell count was 135 cells/mm^3 for the once daily group and 122 cells/mm^3 for the twice daily group.

14.3 Other Studies Supporting Approval in Adult Patients

Study 720: KALETRA twice daily + stavudine + lamivudine

Study 765: KALETRA twice daily + nevirapine + NRTIs

Study 720 (patients without prior antiretroviral therapy) and study 765 (patients with prior protease inhibitor therapy) were randomized, blinded, multi-center trials evaluating treatment with KALETRA at up to three dose levels (200/100 mg twice daily [720 only], 400/100 mg twice daily, and 400/200 mg twice daily). In Study 720, all patients switched to 400/100 mg twice daily between Weeks 48-72. Patients in study 720 had a mean age of 35 years, 70% were Caucasian, and 96% were male, while patients in study 765 had a mean age of 40 years, 73% were Caucasian, and 90% were male. Mean (range) baseline CD4+ cell counts for patients in study 720 and study 765 were 338 (3-918) and 372 (72-807) cells/mm^3, respectively. Mean (range) baseline plasma HIV-1 RNA levels for patients in study 720 and study 765 were 4.9 (3.3 to 6.3) and 4.0 (2.9 to 5.8) log10 copies/mL, respectively.

Through 360 weeks of treatment in study 720, the proportion of patients with HIV-1 RNA < 400 (< 50) copies/mL was 61% (59%) [n = 100]. Among patients completing 360 weeks of treatment with CD4+ cell count measurements [n=60], the mean (median) increase in CD4+ cell count was 501 (457) cells/mm^3. Thirty-nine patients (39%) discontinued the study, including 13 (13%) discontinuations due to adverse reactions and 1 (1%) death.

Through 144 weeks of treatment in study 765, the proportion of patients with HIV-1 RNA < 400 (< 50) copies/mL was 54% (50%) [n = 70], and the corresponding mean increase in CD4+ cell count was 212 cells/mm^3. Twenty-seven patients (39%) discontinued the study, including 5 (7%) discontinuations secondary to adverse reactions and 2 (3%) deaths.

14.4 Pediatric Studies

Study 1030 was an open-label, multicenter, dose-finding trial evaluating the pharmacokinetic profile, tolerability, safety and efficacy of KALETRA oral solution containing lopinavir 80 mg/mL and ritonavir 20 mg/mL at a dose of 300/75 mg/m^2 twice daily plus 2 NRTIs in HIV-1 infected infants ≥14 days and <6 months of age.

Ten infants, ≥14 days and <6 wks of age, were enrolled at a median (range) age of 5.7 (3.6-6.0) weeks and all completed 24 weeks. At entry, median (range) HIV-1 RNA was 6.0 (4.7-7.2) log10 copies/mL. Seven of 10 infants had HIV-1 RNA <400 copies/mL at Week 24. At entry, median (range) CD4+ percentage was 41 (16-59) with a median decrease of 1% (95% CI: -10, 18) from baseline to week 24 in 6 infants with available data.

Twenty-one infants, between 6 weeks and 6 months of age, were enrolled at a median (range) age of 14.7 (6.9-25.7) weeks and 19 of 21 infants completed 24 weeks. At entry, median (range) HIV RNA level was 5.8 (3.7-6.9) log10 copies/mL. Ten of 21 infants had HIV RNA <400 copies/mL at Week 24. At entry, the median (range) CD4+ percentage was 32 (11-54) with a median increase of 4% (95% CI: -1, 9) from baseline to week 24 in 19 infants with available data [see Clinical Pharmacology (12.3) for pharmacokinetic results] .

Study 940 was an open-label, multicenter trial evaluating the pharmacokinetic profile, tolerability, safety and efficacy of KALETRA oral solution containing lopinavir 80 mg/mL and ritonavir 20 mg/mL in 100 antiretroviral naïve (44%) and experienced (56%) pediatric patients. All patients were non-nucleoside reverse transcriptase inhibitor naïve. Patients were randomized to either 230 mg lopinavir/57.5 mg ritonavir per m^2 or 300 mg lopinavir/75 mg ritonavir per m^2. Naïve patients also received lamivudine and stavudine. Experienced patients received nevirapine plus up to two nucleoside reverse transcriptase inhibitors.

Safety, efficacy and pharmacokinetic profiles of the two dose regimens were assessed after three weeks of therapy in each patient. After analysis of these data, all patients were continued on the 300 mg lopinavir/75 mg ritonavir per m^2 dose. Patients had a mean age of 5 years (range 6 months to 12 years) with 14% less than 2 years. Mean baseline CD4+ cell count was 838 cells/mm^3 and mean baseline plasma HIV-1 RNA was 4.7 log10 copies/mL.

Through 48 weeks of therapy, the proportion of patients who achieved and sustained an HIV-1 RNA < 400 copies/mL was 80% for antiretroviral naïve patients and 71% for antiretroviral experienced patients. The mean increase from baseline in CD4+ cell count was 404 cells/mm^3 for antiretroviral naïve and 284 cells/mm^3 for antiretroviral experienced patients treated through 48 weeks. At 48 weeks, two patients (2%) had prematurely discontinued the study. One antiretroviral naïve patient prematurely discontinued secondary to an adverse reaction, while one antiretroviral experienced patient prematurely discontinued secondary to an HIV-1 related event.

Dose selection in pediatric patients was based on the following:

- Among patients 14 days to 6 months of age receiving 300/75 mg/m^2 twice daily without nevirapine, plasma concentrations were lower than those observed in adults or in older children. This dose resulted in HIV-1 RNA < 400 copies/mL in 55% of patients (70% in those initiating treatment at <6 weeks of age).
- Among patients 6 months to 12 years of age, the 230/57.5 mg/m^2 oral solution twice daily regimen without nevirapine and the 300/75 mg/m^2 oral solution twice daily regimen with nevirapine provided lopinavir plasma concentrations similar to those obtained in adult patients receiving the 400/100 mg twice daily regimen (without nevirapine). These doses resulted in treatment benefit (proportion of patients with HIV-1 RNA < 400 copies/mL) similar to that seen in the adult clinical trials.
- Among patients 12 to 18 years of age receiving 400/100 mg/m^2 or 480/120 mg/m^2 (with efavirenz) twice daily, plasma concentrations were 60-100% higher than among 6 to 12 year old patients receiving 230/57.5 mg/m^2. Mean apparent clearance was similar to that observed in adult patients receiving standard dose and in patients 6 to 12 years of age. Although changes in HIV-1 RNA in patients with prior treatment failure were less than anticipated, the pharmacokinetic data supports use of similar dosing as in patients 6 to 12 years of age, not to exceed the recommended adult dose.
- For all age groups, the body surface area dosing was converted to body weight dosing using the patient’s prescribed lopinavir dose.

16 HOW SUPPLIED/STORAGE AND HANDLING

KALETRA® (lopinavir and ritonavir) tablets and oral solution are available in the following strengths and package sizes:

200 mg lopinavir/50 mg ritonavir

Yellow film-coated ovaloid tablets debossed
with the a logo and the code KA

Store KALETRA tablets at 20°- 25°C (68°- 77°F); excursions permitted to 15°- 30°C (59°- 86°F) [see USP controlled room temperature]. Dispense in original container or USP equivalent tight container.
For patient use: exposure of this product to high humidity outside the original container or USP equivalent tight container for longer than 2 weeks is not recommended.

Recommended Storage:

17 PATIENT COUNSELING INFORMATION

Advise the patient to read the FDA-approved patient labeling (Medication Guide)

General Administration Information [see Dosage and Administration (2)] :

- Advise patients to pay special attention to accurate administration of their dose to minimize the risk of accidental overdose or underdose of KALETRA.
- Advise patients and caregivers that the oral solution should be administered using the calibrated dosing cup (supplied) or oral dosing syringe.
- Advise caregivers to inform their healthcare provider if the child’s weight changes in order to make sure that the child’s KALETRA dose is adjusted as needed.
- Inform patients and caregivers that KALETRA tablets may be taken with or without food but KALETRA oral solution should be taken with food to enhance absorption.
- Advise patients to remain under the care of a healthcare provider while using KALETRA and to take KALETRA in combination with other antiretroviral drugs as prescribed.
- Advise patients not to alter the dose or discontinue therapy without consulting with their healthcare provider. If a dose of KALETRA is missed patients should take the dose as soon as possible and then return to their normal schedule. However, if a dose is skipped the patient should not double the next dose.
- Inform patients that it is important to take KALETRA on a regular dosing schedule as directed and to avoid missing doses as that can result in development of resistance.
- Inform patients that there may be a greater chance of developing diarrhea with the once daily regimen as compared with the twice daily regimen.
- Inform patients that Kaletra is not a cure for HIV-1 infection and that they may continue to experience illnesses associated with HIV-1 infection, including opportunistic infections.

Drug Interactions

Inform patients that KALETRA may interact with some drugs; therefore, patients should be advised to report to their healthcare provider the use of any prescription, non-prescription medication or herbal products such as St. John’s Wort [see Contraindications (4), Warnings and Precautions (5.1) and Drug Interactions (7)] .

Pancreatitis

Advise patients that pancreatitis has been observed in patients receiving KALETRA and to alert their healthcare provider if they experience symptoms such as nausea, vomiting or abdominal pain [see Warnings and Precautions (5.3)] .

Skin Rash

Inform patients that skin rash ranging in severity from mild to toxic epidermal necrolysis (TEN), Stevens-Johnson syndrome, erythema multiforme, urticaria, and angioedema have been reported in patients receiving KALETRA or its components lopinavir and/or ritonavir. Advise patients to contact their healthcare provider if they develop a rash while taking KALETRA [see Adverse Reactions (6.1)] .

Hepatotoxicity

Pre-existing liver disease including Hepatitis B or C can worsen with use of KALETRA. This can be seen as worsening of transaminase elevations or hepatic decompensation. Advise patients that their liver function tests will need to be monitored closely especially during the first several months of KALETRA treatment and that they should notify their healthcare provider if they develop the signs and symptoms of worsening liver disease including loss of appetite, abdominal pain, jaundice, and itchy skin [see Warnings and Precautions (5.4)] .

QT and PR Interval Prolongation

Advise patients that KALETRA may produce changes in the electrocardiogram (e.g., PR and/or QT prolongation) and to consult their healthcare provider if they experience symptoms such as dizziness, lightheadedness, abnormal heart rhythm or loss of consciousness [see Warnings and Precautions (5.5, 5.6)] .

Diabetes Mellitus/Hyperglycemia

Advise patients that new onset of diabetes or exacerbation of pre-existing diabetes mellitus, and hyperglycemia have been reported during KALETRA use. Advise patients to notify their healthcare provider if they develop the signs and symptoms of diabetes mellitus including frequent urination, excessive thirst, extreme hunger or unusual weight loss and/or an increased blood sugar while on KALETRA as they may require a change in their diabetes treatment or new treatment [see Warnings and Precautions (5.7)] .

Immune Reconstitution Syndrome

Advise patients that immune reconstitution syndrome has been reported in HIV-infected patients treated with combination antiretroviral therapy, including KALETRA [see Warnings and Precautions (5.8)] .

Lipid Disorders

Advise patients that treatment with KALETRA therapy can result in substantial increases in the concentration of total cholesterol and triglycerides [see Warnings and Precautions (5.9)] .

Fat Redistribution

Advise patients that redistribution or accumulation of body fat may occur in patients receiving antiretroviral therapy and that the cause and long term health effects of these conditions are not known at this time [see Warnings and Precautions (5.10)] .

Patients with Hemophilia

Advise patients with hemophilia that they may experience increased bleeding when treated with protease inhibitors such as KALETRA [see Warnings and Precautions (5.11)] .

Pregnancy Exposure Registry

Inform patients that there is an antiretroviral pregnancy registry that monitors fetal outcomes of pregnant women exposed to KALETRA [see Use in Specific Populations (8.1)] .

Lactation

Instruct women with HIV-1 infection not to breastfeed because HIV-1 can be passed to the baby in breast milk [see Use in Specific Populations (8.2)] .

Manufactured by AbbVie Inc., North Chicago, IL 60064 USA

KALETRA is a trademark of AbbVie Inc.

The brands listed are trademarks of their respective owners and are not trademarks of AbbVie Inc. The makers of these brands are not affiliated with and do not endorse AbbVie Inc. or its products.

© 2020 AbbVie Inc. All rights reserved.

20065455

MEDICATION GUIDE

KALETRA® (kuh-LEE-tra)
(lopinavir and ritonavir)
tablets

KALETRA® (kuh-LEE-tra)
(lopinavir and ritonavir)
oral solution

What is the most important information I should know about KALETRA?

KALETRA may cause serious side effects, including:

- Interactions with other medicines. It is important to know the medicines that should not be taken with KALETRA. For more information, see "Who should not take KALETRA?”
- Side Effects in babies taking KALETRA oral solution. KALETRA oral solution contains alcohol (ethanol) and propylene glycol. Call your healthcare provider right away if your baby appears too sleepy or their breathing changes.
- Inflammation of your pancreas (pancreatitis). KALETRA can cause pancreatitis which may be serious and may lead to death. People who have high levels of a certain fat (triglycerides) have a risk for developing pancreatitis. If you have advanced HIV-1 disease, you may have an increased risk of high triglyceride levels in your blood, and pancreatitis. If you have a history of pancreatitis, you may have an increased risk of it coming back again during treatment with KALETRA. Tell your healthcare provider if you have any signs or symptoms of pancreatitis including:

° nausea ° vomiting ° stomach-area (abdominal) pain

- Liver problems. Liver problems, including death, can happen in people who take KALETRA. Your healthcare provider should do blood tests before and during your treatment with KALETRA to check your liver function. If you have Hepatitis B or Hepatitis C, or other liver problems, you may have an increased risk for developing new or worsening of liver problems during treatment with KALETRA. Tell your healthcare provider right away if you have any signs and symptoms of liver problems including:

- loss of appetite
- yellow skin and whites of eyes (jaundice)
- dark-colored urine

- pale colored stools
- itchy skin
- stomach area (abdominal) pain

- Changes in your heart rhythm and the electrical activity of your heart. These changes may be seen on an EKG (electrocardiogram) and can lead to serious heart problems. Your risk for these problems may be higher if you:
  - have a history of abnormal heart rhythm or certain types of heart problems.
  - take other medicines that can affect your heart rhythm during treatment with KALETRA.

Tell your healthcare provider right away if you have any of these symptoms:

- dizziness
- lightheadedness

- fainting
- sensation of abnormal heartbeats

See “What are the possible side effects of KALETRA?” for more information about serious side effects.

What is KALETRA?
KALETRA is a prescription medicine that is used with other antiretroviral medicines to treat Human Immunodeficiency Virus-1 (HIV-1) infection in adults and children 14 days of age and older.
HIV is the virus that causes AIDS (Acquired Immune Deficiency Syndrome).
It is not known if KALETRA is safe and effective in children under 14 days old.

Who should not take KALETRA?

Do not take KALETRA if you:

- are allergic to lopinavir, ritonavir, or any of the ingredients in KALETRA. See the end of this Medication Guide for a complete list of ingredients in KALETRA.
- if you take any of the following medicines:
  - alfuzosin
  - apalutamide
  - ranolazine
  - dronedarone
  - colchicine, if you have kidney or liver problems.
  - rifampin
  - lurasidone
  - pimozide
  - ergot containing medicines including:
    - dihydroergotamine mesylate
    - ergotamine tartrate
    - methylergonovine
  - cisapride
  - elbasvir/grazoprevir
  - lovastatin
  - simvastatin
  - lomitapide
  - sildenafil (Revatio®), when used for the treatment of pulmonary arterial hypertension
  - triazolam
  - midazolam when taken by mouth
  - St. John’s Wort (Hypericum perforatum®)

Serious problems can happen if you or your child takes any of the medicines listed above with KALETRA.

Before taking KALETRA, tell your healthcare provider about all of your medical conditions, including if you:

- have ever had a serious skin rash or an allergic reaction to medicines that contain lopinavir or ritonavir.
- have or had pancreas problems.
- have liver problems, including Hepatitis B or Hepatitis C.
- have any heart problems, including if you have a condition called Congenital Long QT Syndrome.
- have low potassium in your blood.
- have diabetes.
- have high cholesterol in your blood.
- have hemophilia. KALETRA may cause increased bleeding.
- are pregnant or plan to become pregnant. It is not known if KALETRA will harm your unborn baby.
  - KALETRA oral solution contains alcohol (ethanol) and propylene glycol. You should not take KALETRA oral solution during pregnancy because there is no safe level of alcohol exposure during pregnancy. Tell your healthcare provider if you become pregnant during treatment with KALETRA.
  - KALETRA may reduce how well hormonal birth control works. Females who may become pregnant should use another effective form of birth control or an additional barrier method of birth control during treatment with KALETRA.
  - Pregnancy Registry: There is a pregnancy registry for women who take antiretroviral medicines during pregnancy. The purpose of the pregnancy registry is to collect information about the health of you and your baby. Talk to your healthcare provider about how you can take part in this registry.
- are breastfeeding or plan to breastfeed. Do not breastfeed if you take KALETRA.
  - You should not breastfeed if you have HIV-1 because of the risk of passing HIV-1 to your baby.
  - Talk to your healthcare provider about the best way to feed your baby.

Tell your healthcare provider about all the medicines you take, including prescription and over-the-counter medicines, vitamins, and herbal supplements. Many medicines interact with KALETRA.

Keep a list of your medicines to show your healthcare provider and pharmacist.

You can ask your healthcare provider or pharmacist for a list of medicines that interact with KALETRA.

Do not start taking a new medicine without telling your healthcare provider. Your healthcare provider can tell you if it is safe to take KALETRA with other medicines. Your healthcare provider may need to change the dose of other medicines during treatment with KALETRA.

How should I take KALETRA?

- Take KALETRA every day exactly as prescribed by your healthcare provider.
- Stay under the care of your healthcare provider during treatment with KALETRA.
- It is important to set up a dosing schedule and follow it every day.
- Do not change your treatment or stop treatment without first talking with your healthcare provider.
- Swallow KALETRA tablets whole. Do not chew, break, or crush KALETRA tablets.
- KALETRA tablets can be taken with or without food.
- KALETRA oral solution must be taken with food.
- If you are taking both didanosine and KALETRA:
  - Didanosine can be taken at the same time as KALETRA tablets, without food.
  - Take didanosine either 1 hour before or 2 hours after taking KALETRA oral solution.
- If you are pregnant:
  - You should not take KALETRA tablets on a 1 time each day dose schedule.
  - Avoid use of KALETRA oral solution.
- If your child is prescribed KALETRA:
  - Tell your healthcare provider if your child’s weight changes.
- KALETRA should not be given to children on a 1 time each day dose schedule. When giving KALETRA to your child, give KALETRA exactly as prescribed.
  - Use the dosing cup (supplied) or an oral syringe with mL (milliliter) markings to give the prescribed dose of KALETRA oral solution to your child. Your pharmacist should provide an oral syringe to you.
  - KALETRA oral solution contains propylene glycol and a large amount of alcohol (ethanol). KALETRA oral solution should not be given to babies younger than 14 days of age unless your healthcare provider thinks it is right for your baby.
- Talk with your healthcare provider if you plan to take or give KALETRA oral solution through a feeding tube. KALETRA oral solution contains propylene glycol and alcohol (ethanol), and should not be used with certain feeding tubes.
- You may have a greater chance of getting diarrhea if you take KALETRA 1 time each day than if you take it 2 times each day.
- Do not miss a dose of KALETRA. This could make the virus harder to treat. If you forget to take KALETRA, take the missed dose right away. If it is almost time for your next dose, do not take the missed dose. Instead, follow your regular dosing schedule by taking your next dose at its regular time. Do not take more than one dose of KALETRA at one time.
- If you or your child take more than the prescribed dose of KALETRA, call your healthcare provider or go to the nearest emergency room right away.

What are the possible side effects of KALETRA?
KALETRA can cause serious side effects, including:

- See “What is the most important information I should know about KALETRA?”

- Diabetes and high blood sugar (hyperglycemia). You may develop new or worsening diabetes or high blood sugar during treatment with KALETRA. Tell your healthcare provider if you get any of the following signs or symptoms:

- urinate more often than usual
- increased hunger or thirst

- unusual weight loss
- increase in your blood sugar levels

- Your healthcare provider may need to start you on medicine to treat high blood sugar or change your diabetes medicines.

- Changes in your immune system (Immune Reconstitution Syndrome) can happen when you start taking HIV-1 medicines. Your immune system may get stronger and begin to fight infections that have been hidden in your body for a long time. Call your healthcare provider right away if you start having new symptoms after starting your HIV-1 medicine.
- Increases in certain fat (triglycerides and cholesterol) levels in your blood. Large increases of triglycerides and cholesterol can be seen in blood test results of some people who take KALETRA. Your healthcare provider should do blood tests to check your cholesterol and triglyceride levels before you start taking KALETRA and during your treatment.
- Changes in body fat can happen in some people who take antiretroviral therapy. These changes may include increased amount of fat in the upper back and neck ("buffalo hump"), breast, and around the middle of your body (trunk). Loss of fat from the legs, arms and face may also happen. The exact cause and long-term health effects of these conditions are not known at this time.
- Increased bleeding in people with hemophilia. Some people with hemophilia have increased bleeding with KALETRA or similar medicines.
- Skin rash, which can be severe, can happen in people who take KALETRA. Tell your healthcare provider if you have a history of skin rash with other medicine used to treat your HIV-1 infection or if you get any skin rash during treatment with KALETRA.
- Kidney stones

Common side effects of KALETRA include:

- diarrhea
- nausea

- vomiting
- increased fats in blood (triglycerides or cholesterol)

These are not all of the possible side effects of KALETRA. For more information, ask your healthcare provider or pharmacist.

Call your doctor for medical advice about side effects. You may report side effects to FDA at 1-800-FDA-1088.

How should I store KALETRA?
KALETRA tablets:

- Store KALETRA tablets at room temperature, between 68°F to 77°F (20°C to 25°C).
- Store KALETRA tablets in the original container.
- Do not keep KALETRA tablets out of the container it comes in for longer than 2 weeks, especially in areas where there is a lot of humidity.
- Keep the container closed tightly.

KALETRA oral solution:

- Store KALETRA oral solution in a refrigerator, between 36°F to 46°F (2°C to 8°C). KALETRA oral solution that is kept refrigerated may be used until the expiration date printed on the label.
- KALETRA oral solution that is stored at room temperature (less than 77°F or 25°C) should be used within 2 months.
- Keep KALETRA oral solution away from high heat.
- Throw away any medicine that is out of date or that you no longer need.

Keep KALETRA and all medicines out of the reach of children.

General information about the safe and effective use of KALETRA.
Medicines are sometimes prescribed for purposes other than those listed in a Medication Guide. Do not use KALETRA for a condition for which it was not prescribed. Do not give KALETRA to other people, even if they have the same condition you have. It may harm them.
You can ask your pharmacist or healthcare provider for information about KALETRA that is written for health professionals.

What are the ingredients in KALETRA?
Active ingredients: lopinavir and ritonavir
Inactive ingredients:
KALETRA 200 mg lopinavir and 50 mg ritonavir yellow tablets: colloidal silicon dioxide, copovidone, sodium stearyl fumarate, and sorbitan monolaurate. The film coating contains: colloidal silicone dioxide, hydroxypropyl cellulose, hypromellose, polyethylene glycol 400, polyethylene glycol 3350, polysorbate 80, talc, titanium dioxide, and yellow ferric oxide E172.
KALETRA 200 mg lopinavir and 50 mg ritonavir red tablets: colloidal silicon dioxide, copovidone, sodium stearyl fumarate, and sorbitan monolaurate. The film coating contains: colloidal silicone dioxide, hydroxypropyl cellulose, hypromellose, polyethylene glycol 400, polyethylene glycol 3350, polysorbate 80, talc, titanium dioxide, and red ferric oxide E172.
KALETRA 100 mg lopinavir and 25 mg ritonavir pale yellow tablets: colloidal silicon dioxide, copovidone, sodium stearyl fumarate, and sorbitan monolaurate. The film coating contains: polyethylene glycol 3350, polyvinyl alcohol, talc, titanium dioxide, and yellow ferric oxide E172.
KALETRA 100 mg lopinavir and 25 mg ritonavir pink tablets: colloidal silicon dioxide, copovidone, sodium stearyl fumarate, and sorbitan monolaurate. The film coating contains: polyethylene glycol 3350, polyvinyl alcohol, talc, titanium dioxide, and red ferric oxide E172.
KALETRA oral solution: acesulfame potassium, artificial cotton candy flavor, citric acid, ethanol (a type of alcohol), glycerin, high fructose corn syrup, Magnasweet-110 flavor, menthol, natural and artificial vanilla flavor, peppermint oil, polyoxyl 40 hydrogenated castor oil, povidone, propylene glycol, saccharin sodium, sodium chloride, sodium citrate, and water.
KALETRA oral solution contains approximately 42% ethanol (a type of alcohol) and approximately 15% propylene glycol. “See How should I take KALETRA?”
For more information about KALETRA call 1-800-633-9110 or go to www.KALETRA.com
Manufactured by AbbVie Inc., North Chicago, IL 60064 USA
KALETRA is a trademark of AbbVie Inc. © 2020 AbbVie Inc. All rights reserved.
The brands listed are trademarks of their respective owners and are not trademarks of AbbVie Inc. The makers of these brands are not affiliated with and do not endorse AbbVie Inc. or its products.
20065455

This Medication Guide has been approved by the U.S. Food and Drug Administration.
Revised: October 2020